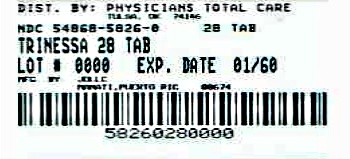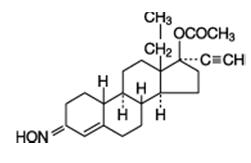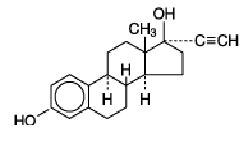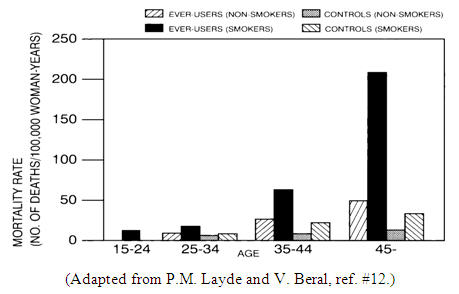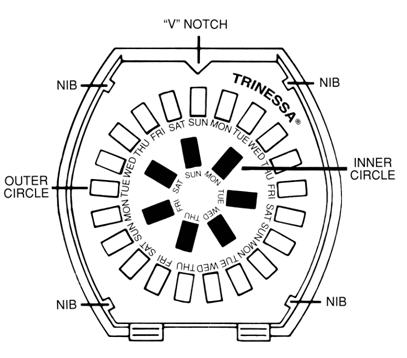 DRUG LABEL: TriNessa
NDC: 54868-5826 | Form: KIT | Route: ORAL
Manufacturer: Physicians Total Care, Inc.
Category: prescription | Type: HUMAN PRESCRIPTION DRUG LABEL
Date: 20120523

ACTIVE INGREDIENTS: norgestimate 0.18 mg/1 1; ethinyl estradiol 0.035 mg/1 1; norgestimate 0.215 mg/1 1; ethinyl estradiol 0.035 mg/1 1; norgestimate 0.25 mg/1 1; ethinyl estradiol 0.035 mg/1 1
INACTIVE INGREDIENTS: CARNAUBA WAX; CROSCARMELLOSE SODIUM; HYPROMELLOSES; LACTOSE; MAGNESIUM STEARATE; CELLULOSE, MICROCRYSTALLINE; POLYETHYLENE GLYCOLS; TITANIUM DIOXIDE; WATER; FD&C BLUE No. 2; ALUMINUM OXIDE; CARNAUBA WAX; CROSCARMELLOSE SODIUM; HYPROMELLOSES; LACTOSE; MAGNESIUM STEARATE; CELLULOSE, MICROCRYSTALLINE; POLYETHYLENE GLYCOLS; TITANIUM DIOXIDE; WATER; FD&C BLUE No. 2; ALUMINUM OXIDE; CARNAUBA WAX; CROSCARMELLOSE SODIUM; HYPROMELLOSES; LACTOSE; MAGNESIUM STEARATE; CELLULOSE, MICROCRYSTALLINE; POLYETHYLENE GLYCOLS; POLYSORBATE 80; TITANIUM DIOXIDE; WATER; FD&C BLUE NO. 2; ALUMINUM OXIDE; FERRIC OXIDE RED; HYPROMELLOSES; LACTOSE; MAGNESIUM STEARATE; POLYETHYLENE GLYCOLS; STARCH, CORN; TALC; TITANIUM DIOXIDE; WATER

TriNessa® Tablets
(norgestimate and ethinyl estradiol)

Patients should be counseled that this product does not protect against HIV infection (AIDS) and other sexually transmitted diseases.

DESCRIPTION

The following product is a combination oral contraceptive containing the progestational compound norgestimate and the estrogenic compound ethinyl estradiol.

TriNessa® Tablets

Each white tablet contains 0.180 mg of the progestational compound, norgestimate (18,19-Dinor-17-pregn-4-en-20-yn-3-one,17-(acetyloxy)-13-ethyl-,oxime,(17α)-(+)-) and 0.035 mg of the estrogenic compound, ethinyl estradiol (19-nor-17α-pregna,1,3,5(10)-trien-20-yne-3,17-diol). Inactive ingredients include carnauba wax, croscarmellose sodium, hypromellose, lactose, magnesium stearate, microcrystalline cellulose, polyethylene glycol, purified water and titanium dioxide.

Each light blue tablet contains 0.215 mg of the progestational compound norgestimate (18,19-Dinor-17-pregn-4-en-20-yn-3-one,17-(acetyloxy)-13-ethyl-,oxime,(17α)-(+)-) and 0.035 mg of the estrogenic compound, ethinyl estradiol (19-nor-17α-pregna,1,3,5(10)-trien-20-yne-3,17-diol). Inactive ingredients include FD & C Blue No. 2 Aluminum Lake, carnauba wax, croscarmellose sodium, hypromellose, lactose, magnesium stearate, microcrystalline cellulose, polyethylene glycol, purified water and titanium dioxide.

Each blue tablet contains 0.250 mg of the progestational compound norgestimate (18,19-Dinor-17-pregn-4-en-20-yn-3-one,17-(acetyloxy)-13-ethyl-,oxime,(17α)-(+)-) and 0.035 mg of the estrogenic compound, ethinyl estradiol (19-nor-17α-pregna,1,3,5(10)-trien-20-yne-3,17-diol). Inactive ingredients include FD & C Blue No. 2 Aluminum Lake, carnauba wax, croscarmellose sodium, hypromellose, lactose, magnesium stearate, microcrystalline cellulose, polyethylene glycol, polysorbate 80, purified water and titanium dioxide.

Each dark green tablet contains only inert ingredients, as follows: FD & C Blue No. 2 Aluminum Lake, ferric oxide, hypromellose, lactose, magnesium stearate, polyethylene glycol, pregelatinized corn starch, purified water, talc and titanium dioxide.

Nogestimate
Ethinyl Estradiol

CLINICAL PHARMACOLOGY

Oral Contraception

Combination oral contraceptives act by suppression of gonadotropins. Although the primary mechanism of this action is inhibition of ovulation, other alterations include changes in the cervical mucus (which increase the difficulty of sperm entry into the uterus) and the endometrium (which reduce the likelihood of implantation).

Receptor binding studies, as well as studies in animals and humans, have shown that norgestimate and 17-deacetyl norgestimate, the major serum metabolite, combine high progestational activity with minimal intrinsic androgenicity.^90–93 Norgestimate, in combination with ethinyl estradiol, does not counteract the estrogen-induced increases in sex hormone binding globulin (SHBG), resulting in lower serum testosterone.^90,91,94

Acne

Acne is a skin condition with a multifactorial etiology, including androgen stimulation of sebum production. While the combination of ethinyl estradiol and norgestimate increases sex hormone binding globulin (SHBG) and decreases free testosterone, the relationship between these changes and a decrease in the severity of facial acne in otherwise healthy women with this skin condition has not been established.

PHARMACOKINETICS

Absorption

Norgestimate (NGM) and ethinyl estradiol (EE) are rapidly absorbed following oral administration. Norgestimate is rapidly and completely metabolized by first pass (intestinal and/or hepatic) mechanisms to norelgestromin (NGMN) and norgestrel (NG), which are the major active metabolites of norgestimate.

Peak serum concentrations of NGMN and EE are generally reached by 2 hours after administration of TriNessa®. Accumulation following multiple dosing of the 250 mcg NGM / 35 mcg dose is approximately 2-fold for NGMN and EE compared with single dose administration. The pharmacokinetics of NGMN is dose proportional following NGM doses of 180 mcg to 250 mcg. Steady-state concentration of EE is achieved by Day 7 of each dosing cycle. Steady-state concentrations of NGMN and NG are achieved by Day 21. Non-linear accumulation (approximately 8 fold) of norgestrel is observed as a result of high affinity binding to SHBG (sex hormone-binding globulin), which limits its biological activity.

Table 1. Summary of norelgestromin, norgestrel and ethinyl estradiol pharmacokinetic parameters.
Mean (SD) Pharmacokinetic Parameters of TriNessa® During a Three Cycle Study
Analyte | Cycle | Day | Cmax | tmax (h) | AUC0–24h | t1/2 (h)
NGMN | 3 | 7 | 1.80 (0.46) | 1.42 (0.73) | 15.0 (3.88) | NC
 |  | 14 | 2.12 (0.56) | 1.21 (0.26) | 16.1 (4.97) | NC
 |  | 21 | 2.66 (0.47) | 1.29 (0.26) | 21.4 (3.46) | 22.3 (6.54)
NG | 3 | 7 | 1.94 (0.82) | 3.15 (4.05) | 34.8 (16.5) | NC
 |  | 14 | 3.00 (1.04) | 2.21 (2.03) | 55.2 (23.5) | NC
 |  | 21 | 3.66 (1.15) | 2.58 (2.97) | 69.3 (23.8) | 40.2 (15.4)
EE | 3 | 7 | 124 (39.5) | 1.27 (0.26) | 1130 (420) | NC
 |  | 14 | 128 (38.4) | 1.32 (0.25) | 1130 (324) | NC
 |  | 21 | 126 (34.7) | 1.31 (0.56) | 1090 (359) | 15.9 (4.39)
Cmax = peak serum concentration, tmax = time to reach peak serum concentration, AUC0–24h = area under serum concentration vs time curve from 0 to 24 hours, t1/2 = elimination half-life, NC = not calculated.
NGMN and NG: Cmax = ng/mL, AUC0–24h=h∙ng/mL
EE: Cmax=pg/mL, AUC0–24h=h∙pg/mL

The effect of food on the pharmacokinetics of TriNessa® has not been studied.

Distribution

Norelgestromin and norgestrel are highly bound (>97%) to serum proteins. Norelgestromin is bound to albumin and not to SHBG, while norgestrel is bound primarily to SHBG. Ethinyl estradiol is extensively bound (>97%) to serum albumin and induces an increase in the serum concentrations of SHBG.

Metabolism

Norgestimate is extensively metabolized by first-pass mechanisms in the gastrointestinal tract and/or liver. Norgestimate's primary active metabolite is norelgestromin. Subsequent hepatic metabolism of norelgestromin occurs and metabolites include norgestrel, which is also active, and various hydroxylated and conjugated metabolites. Ethinyl estradiol is also metabolized to various hydroxylated products and their glucuronide and sulfate conjugates.

Excretion

The metabolites of norelgestromin and ethinyl estradiol are eliminated by renal and fecal pathways. Following administration of ^14C-norgestimate, 47% (45–49%) and 37% (16–49%) of the administered radioactivity was eliminated in the urine and feces, respectively. Unchanged norgestimate was not detected in the urine. In addition to 17-deacetyl norgestimate, a number of metabolites of norgestimate have been identified in human urine following administration of radiolabeled norgestimate. These include 18, 19-Dinor-17-pregn-4-en-20-yn-3-one,17-hydroxy-13-ethyl,(17α)-(-);18,19-Dinor-5β-17-pregnan-20-yn,3α,17β-dihydroxy-13-ethyl,(17α), various hydroxylated metabolites and conjugates of these metabolites.

Special Populations

The effects of body weight, body surface area or age on the pharmacokinetics of TriNessa® have not been studied.

Hepatic Impairment

The effects of hepatic impairment on the pharmacokinetics of TriNessa® have not been studied. However, steroid hormones may be poorly metabolized in women with impaired liver function (see PRECAUTIONS).

Renal Impairment

The effects of renal impairment on the pharmacokinetics of TriNessa® have not been studied.

Drug-Drug Interactions

No formal drug-drug interaction studies were conducted with TriNessa®. Interactions between contraceptive steroids and other drugs have been reported in the literature (see PRECAUTIONS).

Although norelgestromin and its metabolites inhibit a variety of P450 enzymes in human liver microsomes, under the recommended dosing regimen, the in vivo concentrations of norelgestromin and its metabolites, even at the peak serum levels, are relatively low compared to the inhibitory constant (Ki).

INDICATIONS AND USAGE

TriNessa® is indicated for the prevention of pregnancy in women who elect to use oral contraceptives as a method of contraception.

TriNessa® is indicated for the treatment of moderate acne vulgaris in females at least 15 years of age, who have no known contraindications to oral contraceptive therapy and have achieved menarche. TriNessa® should be used for the treatment of acne only if the patient desires an oral contraceptive for birth control.

Oral contraceptives are highly effective for pregnancy prevention. Table II lists the typical accidental pregnancy rates for users of combination oral contraceptives and other methods of contraception. The efficacy of these contraceptive methods, except sterilization, the IUD, and the Norplant® System, depends upon the reliability with which they are used. Correct and consistent use of methods can result in lower failure rates.

Table II: Percentage of Women Experiencing an Unintended Pregnancy During the First Year of Typical Use and the First Year of Perfect Use of Contraception and the Percentage Continuing Use at the End of the First Year. United States.
 | % of Women Experiencing an Unintended Pregnancy within the First Year of Use |  | % of Women Continuing Use at One Year
Method | Typical Use | Perfect Use
(1) | (2) | (3) | (4)
Chance | 85 | 85
Spermicides | 26 | 6 | 40
Periodic abstinence | 25 |  | 63
Calendar |  | 9
Ovulation Method |  | 3
Sympto-Thermal |  | 2
Post-Ovulation |  | 1
Cap [With spermicidal cream or jelly.]
Parous Women | 40 | 26 | 42
Nulliparous Women | 20 | 9 | 56
Sponge
Parous Women | 40 | 20 | 42
Nulliparous Women | 20 | 9 | 56
Diaphragm | 20 | 6 | 56
Withdrawal | 19 | 4
Condom
Female (Reality®) | 21 | 5 | 56
Male | 14 | 3 | 61
Pill | 5 |  | 71
Progestin Only |  | 0.5
Combined |  | 0.1
IUD
Progesterone T | 2.0 | 1.5 | 81
Copper T380A | 0.8 | 0.6 | 78
LNg 20 | 0.1 | 0.1 | 81
Depo-Provera® | 0.3 | 0.3 | 70
Norplant® and Norplant-2® | 0.05 | 0.05 | 88
Female Sterilization | 0.5 | 0.5 | 100
Male Sterilization | 0.15 | 0.10 | 100
Hatcher et al, 1998, Ref. #1.
Emergency Contraceptive Pills: Treatment initiated within 72 hours after unprotected intercourse reduces the risk of pregnancy by at least 75%. [The treatment schedule is one dose within 72 hours after unprotected intercourse, and a second dose 12 hours after the first dose. The Food and Drug Administration has declared the following brands of oral contraceptives to be safe and effective for emergency contraception: Ovral® (1 dose is 2 white pills), Alesse® (1 dose is 5 pink pills), Nordette® or Levlen® (1 dose is 2 light-orange pills), Lo/Ovral® (1 dose is 4 white pills), Triphasil® or Tri-Levlen® (1 dose is 4 yellow pills).]
Lactational Amenorrhea Method: LAM is a highly effective, temporary method of contraception. [However, to maintain effective protection against pregnancy, another method of contraception must be used as soon as menstruation resumes, the frequency or duration of breastfeeds is reduced, bottle feeds are introduced, or the baby reaches six months of age.]
Source: Trussell J, Contraceptive efficacy. In Hatcher RA, Trussell J, Stewart F, Cates W, Stewart GK, Kowal D, Guest F, Contraceptive Technology: Seventeenth Revised Edition. New York NY: Irvington Publishers, 1998.

TriNessa® has not been studied for and is not indicated for use in emergency contraception.

In four clinical trials with TriNessa®, a total of 4,756 subjects completed 45,244 cycles, and the use-efficacy pregnancy rate was approximately 1 pregnancy per 100 women-years.

TriNessa® was evaluated for the treatment of acne vulgaris in two randomized, double-blind, placebo-controlled, multicenter, Phase 3, six (28 day) cycle studies. 221 patients received TriNessa® and 234 patients received placebo. Mean age at enrollment for both groups was 28 years. At the end of 6 months, the mean total lesion count changes from 55 to 31 (42% reduction) in patients treated with TriNessa® and from 54 to 38 (27% reduction) in patients similarly treated with placebo. Table III summarizes the changes in lesion count for each type of lesion in the ITT population. Based on the investigator's global assessment conducted at the final visit, patients treated with TriNessa® showed a statistically significant improvement in total lesions compared to those treated with placebo.

Table III: Acne Vulgaris Indication. Combined Results: Two Multicenter, Placebo-Controlled Trials. Observed Means at Six Months (LOCF) [LOCF: Last Observation Carried Forward] and at Baseline. Intent-to-Treat Population.
 | TriNessa® (N=221) |  | Placebo (N=234) |  | Difference in Counts between TriNessa® and Placebo at 6 Months
# of Lesions | Counts | % Reduction | Counts | % Reduction
INFLAMMATORY LESIONS
Baseline Mean | 19 |  | 19
Sixth Month Mean | 10 | 48% | 13 | 30% | 3 (95%CI: -1.2, 5.1)
NON-INFLAMMATORY LESIONS
Baseline Mean | 36 |  | 35
Sixth Month Mean | 22 | 34% | 25 | 21% | 3 (95% CI: -0.2, 7.8)
TOTAL LESIONS
Baseline Mean | 55 |  | 54
Sixth Month Mean | 31 | 42% | 38 | 27% | 7 (95% CI: 2.0, 11.9)

CONTRAINDICATIONS

Oral contraceptives should not be used in women who currently have the following conditions:

- Thrombophlebitis or thromboembolic disorders
- A past history of deep vein thrombophlebitis or thromboembolic disorders
- Cerebral vascular or coronary artery disease (current or past history)
- Valvular heart disease with complications
- Severe hypertension
- Diabetes with vascular involvement
- Headaches with focal neurological symptoms
- Major surgery with prolonged immobilization
- Known or suspected carcinoma of the breast or personal history of breast cancer
- Carcinoma of the endometrium or other known or suspected estrogen-dependent neoplasia
- Undiagnosed abnormal genital bleeding
- Cholestatic jaundice of pregnancy or jaundice with prior pill use
- Acute or chronic hepatocellular disease with abnormal liver function
- Hepatic adenomas or carcinomas
- Known or suspected pregnancy
- Hypersensitivity to any component of this product

WARNINGS

BOXED WARNING

Cigarette smoking increases the risk of serious cardiovascular side effects from oral contraceptive use. This risk increases with age and with heavy smoking (15 or more cigarettes per day) and is quite marked in women over 35 years of age. Women who use oral contraceptives should be strongly advised not to smoke.

The use of oral contraceptives is associated with increased risks of several serious conditions including myocardial infarction, thromboembolism, stroke, hepatic neoplasia, and gallbladder disease, although the risk of serious morbidity or mortality is very small in healthy women without underlying risk factors. The risk of morbidity and mortality increases significantly in the presence of other underlying risk factors such as hypertension, hyperlipidemias, obesity and diabetes.

Practitioners prescribing oral contraceptives should be familiar with the following information relating to these risks.

The information contained in this package insert is principally based on studies carried out in patients who used oral contraceptives with higher formulations of estrogens and progestogens than those in common use today. The effect of long-term use of the oral contraceptives with lower formulations of both estrogens and progestogens remains to be determined.

Throughout this labeling, epidemiological studies reported are of two types: retrospective or case control studies and prospective or cohort studies. Case control studies provide a measure of the relative risk of a disease, namely, a ratio of the incidence of a disease among oral contraceptive users to that among nonusers. The relative risk does not provide information on the actual clinical occurrence of a disease. Cohort studies provide a measure of attributable risk, which is the difference in the incidence of disease between oral contraceptive users and nonusers. The attributable risk does provide information about the actual occurrence of a disease in the population (adapted from refs. 2 and 3 with the author's permission). For further information, the reader is referred to a text on epidemiological methods.

1. Thromboembolic Disorders and Other Vascular Problems

a. Myocardial Infarction

An increased risk of myocardial infarction has been attributed to oral contraceptive use. This risk is primarily in smokers or women with other underlying risk factors for coronary artery disease such as hypertension, hypercholesterolemia, morbid obesity, and diabetes. The relative risk of heart attack for current oral contraceptive users has been estimated to be two to six.^4–10 The risk is very low under the age of 30.

Smoking in combination with oral contraceptive use has been shown to contribute substantially to the incidence of myocardial infarctions in women in their mid-thirties or older with smoking accounting for the majority of excess cases.^11 Mortality rates associated with circulatory disease have been shown to increase substantially in smokers, especially in those 35 years of age and older, and in nonsmokers over the age of 40 among women who use oral contraceptives.

Figure 1. Circulatory Disease Mortality Rates per 100,000 Women-Years by Age, Smoking Status and Oral Contraceptive Use

Oral contraceptives may compound the effects of well-known risk factors, such as hypertension, diabetes, hyperlipidemias, age and obesity.^13 In particular, some progestogens are known to decrease HDL cholesterol and cause glucose intolerance, while estrogens may create a state of hyperinsulinism.^14–18 Oral contraceptives have been shown to increase blood pressure among users (see Section 9 in WARNINGS). Similar effects on risk factors have been associated with an increased risk of heart disease. Oral contraceptives must be used with caution in women with cardiovascular disease risk factors.

Norgestimate has minimal androgenic activity (see CLINICAL PHARMACOLOGY), and there is some evidence that the risk of myocardial infarction associated with oral contraceptives is lower when the progestogen has minimal androgenic activity than when the activity is greater.^97

b. Thromboembolism

An increased risk of thromboembolic and thrombotic disease associated with the use of oral contraceptives is well established. Case control studies have found the relative risk of users compared to nonusers to be 3 for the first episode of superficial venous thrombosis, 4 to 11 for deep vein thrombosis or pulmonary embolism, and 1.5 to 6 for women with predisposing conditions for venous thromboembolic disease.^2,3,19–24 Cohort studies have shown the relative risk to be somewhat lower, about 3 for new cases and about 4.5 for new cases requiring hospitalization.^25 The risk of thromboembolic disease associated with oral contraceptives is not related to length of use and disappears after pill use is stopped.^2

A two- to four-fold increase in relative risk of post-operative thromboembolic complications has been reported with the use of oral contraceptives.^9 The relative risk of venous thrombosis in women who have predisposing conditions is twice that of women without such medical conditions.^26 If feasible, oral contraceptives should be discontinued at least four weeks prior to and for two weeks after elective surgery of a type associated with an increase in risk of thromboembolism and during and following prolonged immobilization. Since the immediate postpartum period is also associated with an increased risk of thromboembolism, oral contraceptives should be started no earlier than four weeks after delivery in women who elect not to breastfeed.

c. Cerebrovascular Diseases

Oral contraceptives have been shown to increase both the relative and attributable risks of cerebrovascular events (thrombotic and hemorrhagic strokes), although, in general, the risk is greatest among older (>35 years), hypertensive women who also smoke. Hypertension was found to be a risk factor for both users and nonusers, for both types of strokes, and smoking interacted to increase the risk of stroke.^27–29

In a large study, the relative risk of thrombotic strokes has been shown to range from 3 for normotensive users to 14 for users with severe hypertension.^30 The relative risk of hemorrhagic stroke is reported to be 1.2 for non-smokers who used oral contraceptives, 2.6 for smokers who did not use oral contraceptives, 7.6 for smokers who used oral contraceptives, 1.8 for normotensive users and 25.7 for users with severe hypertension.^30 The attributable risk is also greater in older women.^3

d. Dose-Related Risk of Vascular Disease From Oral Contraceptives

A positive association has been observed between the amount of estrogen and progestogen in oral contraceptives and the risk of vascular disease.^31–33 A decline in serum high density lipoproteins (HDL) has been reported with many progestational agents.^14–16 A decline in serum high density lipoproteins has been associated with an increased incidence of ischemic heart disease. Because estrogens increase HDL cholesterol, the net effect of an oral contraceptive depends on a balance achieved between doses of estrogen and progestogen and the activity of the progestogen used in the contraceptives. The activity and amount of both hormones should be considered in the choice of an oral contraceptive.

Minimizing exposure to estrogen and progestogen is in keeping with good principles of therapeutics. For any particular estrogen/progestogen combination, the dosage regimen prescribed should be one which contains the least amount of estrogen and progestogen that is compatible with a low failure rate and the needs of the individual patient. New acceptors of oral contraceptive agents should be started on preparations containing the lowest estrogen content which is judged appropriate for the individual patient.

e. Persistence of Risk of Vascular Disease

There are two studies which have shown persistence of risk of vascular disease for ever-users of oral contraceptives. In a study in the United States, the risk of developing myocardial infarction after discontinuing oral contraceptives persists for at least 9 years for women 40–49 years who had used oral contraceptives for five or more years, but this increased risk was not demonstrated in other age groups.^8 In another study in Great Britain, the risk of developing cerebrovascular disease persisted for at least 6 years after discontinuation of oral contraceptives, although excess risk was very small.^34 However, both studies were performed with oral contraceptive formulations containing 50 micrograms or higher of estrogens.

2. Estimates of Mortality From Contraceptive Use

One study gathered data from a variety of sources which have estimated the mortality rate associated with different methods of contraception at different ages (Table IV). These estimates include the combined risk of death associated with contraceptive methods plus the risk attributable to pregnancy in the event of method failure. Each method of contraception has its specific benefits and risks. The study concluded that with the exception of oral contraceptive users 35 and older who smoke, and 40 and older who do not smoke, mortality associated with all methods of birth control is low and below that associated with childbirth. The observation of an increase in risk of mortality with age for oral contraceptive users is based on data gathered in the 1970's.^35 Current clinical recommendation involves the use of lower estrogen dose formulations and a careful consideration of risk factors. In 1989, the Fertility and Maternal Health Drugs Advisory Committee was asked to review the use of oral contraceptives in women 40 years of age and over. The Committee concluded that although cardiovascular disease risks may be increased with oral contraceptive use after age 40 in healthy non-smoking women (even with the newer low-dose formulations), there are also greater potential health risks associated with pregnancy in older women and with the alternative surgical and medical procedures which may be necessary if such women do not have access to effective and acceptable means of contraception. The Committee recommended that the benefits of low-dose oral contraceptive use by healthy non-smoking women over 40 may outweigh the possible risks.

Of course, older women, as all women, who take oral contraceptives, should take an oral contraceptive which contains the least amount of estrogen and progestogen that is compatible with a low failure rate and individual patient needs.

Table IV: Annual Number of Birth-Related or Method-Related Deaths Associated with Control of Fertility per 100,000 Non-Sterile Women, by Fertility Control Method According to Age
Method of control and outcome | 15–19 | 20–24 | 25–29 | 30–34 | 35–39 | 40–44
No fertility control methods [Deaths are birth-related] | 7.0 | 7.4 | 9.1 | 14.8 | 25.7 | 28.2
Oral contraceptives non-smoker [Deaths are method-related] | 0.3 | 0.5 | 0.9 | 1.9 | 13.8 | 31.6
Oral contraceptives, smoker | 2.2 | 3.4 | 6.6 | 13.5 | 51.1 | 117.2
IUD | 0.8 | 0.8 | 1.0 | 1.0 | 1.4 | 1.4
Condom | 1.1 | 1.6 | 0.7 | 0.2 | 0.3 | 0.4
Diaphragm/spermicide | 1.9 | 1.2 | 1.2 | 1.3 | 2.2 | 2.8
Periodic abstinence | 2.5 | 1.6 | 1.6 | 1.7 | 2.9 | 3.6
Adapted from H.W. Ory, ref. #35.

3. Carcinoma of the Reproductive Organs and Breasts

Numerous epidemiological studies have been performed on the incidence of breast, endometrial, ovarian, and cervical cancer in women using oral contraceptives. The risk of having breast cancer diagnosed may be slightly increased among current and recent users of combination oral contraceptives (COCs). However, this excess risk appears to decrease over time after COC discontinuation and by 10 years after cessation the increased risk disappears. Some studies report an increased risk with duration of use while other studies do not and no consistent relationships have been found with dose or type of steroid. Some studies have found a small increase in risk for women who first use COCs before age 20. Most studies show a similar pattern of risk with COC use regardless of a woman's reproductive history or her family breast cancer history.

Breast cancers diagnosed in current or previous oral contraceptive users tend to be less clinically advanced than in nonusers. Women who currently have or have had breast cancer should not use oral contraceptives because breast cancer is usually a hormonally-sensitive tumor.

Some studies suggest that oral contraceptive use has been associated with an increase in the risk of cervical intraepithelial neoplasia in some populations of women.^45–48 However, there continues to be controversy about the extent to which such findings may be due to differences in sexual behavior and other factors. In spite of many studies of the relationship between oral contraceptive use and breast and cervical cancers, a cause-and-effect relationship has not been established.

4. Hepatic Neoplasia

Benign hepatic adenomas are associated with oral contraceptive use, although the incidence of benign tumors is rare in the United States. Indirect calculations have estimated the attributable risk to be in the range of 3.3 cases/100,000 for users, a risk that increases after four or more years of use especially with oral contraceptives of higher dose.^49 Rupture of benign, hepatic adenomas may cause death through intra-abdominal hemorrhage.^50,51

Studies from Britain have shown an increased risk of developing hepatocellular carcinoma in long-term (>8 years) oral contraceptive users. However, these cancers are extremely rare in the U.S. and the attributable risk (the excess incidence) of liver cancers in oral contraceptive users approaches less than one per million users.

5. Ocular Lesions

There have been clinical case reports of retinal thrombosis associated with the use of oral contraceptives. Oral contraceptives should be discontinued if there is unexplained partial or complete loss of vision; onset of proptosis or diplopia; papilledema; or retinal vascular lesions. Appropriate diagnostic and therapeutic measures should be undertaken immediately.

6. Oral Contraceptive Use Before or During Early Pregnancy

Extensive epidemiological studies have revealed no increased risk of birth defects in women who have used oral contraceptives prior to pregnancy.^56,57 The majority of recent studies also do not indicate a teratogenic effect, particularly in so far as cardiac anomalies and limb reduction defects are concerned^55,56,58,59, when taken inadvertently during early pregnancy.

The administration of oral contraceptives to induce withdrawal bleeding should not be used as a test for pregnancy. Oral contraceptives should not be used during pregnancy to treat threatened or habitual abortion.

It is recommended that for any patient who has missed two consecutive periods, pregnancy should be ruled out. If the patient has not adhered to the prescribed schedule, the possibility of pregnancy should be considered at the time of the first missed period. Oral contraceptive use should be discontinued if pregnancy is confirmed.

7. Gallbladder Disease

Earlier studies have reported an increased lifetime relative risk of gallbladder surgery in users of oral contraceptives and estrogens.^60,61 More recent studies, however, have shown that the relative risk of developing gallbladder disease among oral contraceptive users may be minimal.^62–64 The recent findings of minimal risk may be related to the use of oral contraceptive formulations containing lower hormonal doses of estrogens and progestogens.

8. Carbohydrate and Lipid Metabolic Effects

Oral contraceptives have been shown to cause a decrease in glucose tolerance in a significant percentage of users.^17 This effect has been shown to be directly related to estrogen dose.^65 Progestogens increase insulin secretion and create insulin resistance, this effect varying with different progestational agents.^17,66 However, in the non-diabetic woman, oral contraceptives appear to have no effect on fasting blood glucose.^67 Because of these demonstrated effects, prediabetic and diabetic women in particular should be carefully monitored while taking oral contraceptives.

A small proportion of women will have persistent hypertriglyceridemia while on the pill. As discussed earlier (see WARNINGS 1a and 1d), changes in serum triglycerides and lipoprotein levels have been reported in oral contraceptive users.

In clinical studies with TriNessa® there were no clinically significant changes in fasting blood glucose levels. Minimal statistically significant changes were noted in glucose levels over 24 cycles of use. Glucose tolerance tests showed no clinically significant changes from baseline to cycles 3, 12, and 24.

9. Elevated Blood Pressure

Women with significant hypertension should not be started on hormonal contraception.^98 An increase in blood pressure has been reported in women taking oral contraceptives^68 and this increase is more likely in older oral contraceptive users^69 and with extended duration of use.^61 Data from the Royal College of General Practitioners^12 and subsequent randomized trials have shown that the incidence of hypertension increases with increasing progestational activity.

Women with a history of hypertension or hypertension-related diseases, or renal disease^70 should be encouraged to use another method of contraception. If women elect to use oral contraceptives, they should be monitored closely and if significant elevation of blood pressure occurs, oral contraceptives should be discontinued. For most women, elevated blood pressure will return to normal after stopping oral contraceptives, and there is no difference in the occurrence of hypertension between former and never users.^68–71

10. Headache

The onset or exacerbation of migraine or development of headache with a new pattern which is recurrent, persistent or severe requires discontinuation of oral contraceptives and evaluation of the cause.

11. Bleeding Irregularities

Breakthrough bleeding and spotting are sometimes encountered in patients on oral contraceptives, especially during the first three months of use. Non-hormonal causes should be considered and adequate diagnostic measures taken to rule out malignancy or pregnancy in the event of breakthrough bleeding, as in the case of any abnormal vaginal bleeding. If pathology has been excluded, time or a change to another formulation may solve the problem. In the event of amenorrhea, pregnancy should be ruled out.

Some women may encounter post-pill amenorrhea or oligomenorrhea, especially when such a condition was preexistent.

12. Ectopic Pregnancy

Ectopic as well as intrauterine pregnancy may occur in contraceptive failures.

PRECAUTIONS

1. General

Patients should be counseled that this product does not protect against HIV infection (AIDS) and other sexually transmitted diseases.

2. Physical Examination and Follow-up

It is good medical practice for all women to have annual history and physical examinations, including women using oral contraceptives. The physical examination, however, may be deferred until after initiation of oral contraceptives if requested by the woman and judged appropriate by the clinician. The physical examination should include special reference to blood pressure, breasts, abdomen and pelvic organs, including cervical cytology, and relevant laboratory tests. In case of undiagnosed, persistent or recurrent abnormal vaginal bleeding, appropriate measures should be conducted to rule out malignancy. Women with a strong family history of breast cancer or who have breast nodules should be monitored with particular care.

3. Lipid Disorders

Women who are being treated for hyperlipidemias should be followed closely if they elect to use oral contraceptives. Some progestogens may elevate LDL levels and may render the control of hyperlipidemias more difficult.

4. Liver Function

If jaundice develops in any woman receiving such drugs, the medication should be discontinued. Steroid hormones may be poorly metabolized in patients with impaired liver function.

5. Fluid Retention

Oral contraceptives may cause some degree of fluid retention. They should be prescribed with caution, and only with careful monitoring, in patients with conditions which might be aggravated by fluid retention.

6. Emotional Disorders

Women with a history of depression should be carefully observed and the drug discontinued if depression recurs to a serious degree.

7. Contact Lenses

Contact lens wearers who develop visual changes or changes in lens tolerance should be assessed by an ophthalmologist.

8. Drug Interactions

Changes in contraceptive effectiveness associated with co-administration of other products

Contraceptive effectiveness may be reduced when hormonal contraceptives are co-administered with antibiotics, anticonvulsants, and other drugs that increase the metabolism of contraceptive steroids. This could result in unintended pregnancy or breakthrough bleeding. Examples include rifampin, barbiturates, phenylbutazone, phenytoin, carbamazepine, felbamate, oxcarbazepine, topiramate, griseofulvin and bosentan.

Several of the anti-HIV protease inhibitors have been studied with co-administration of oral combination hormonal contraceptives; significant changes (increase and decrease) in the plasma levels of the estrogen and progestin have been noted in some cases. The safety and efficacy of oral contraceptive products may be affected with co-administration of anti-HIV protease inhibitors. Healthcare professionals should refer to the label of the individual anti-HIV protease inhibitors for further drug-drug interaction information.

Herbal products containing St. John's Wort (hypericum perforatum) may induce hepatic enzymes (cytochrome P450) and p-glycoprotein transporter and may reduce the effectiveness of contraceptive steroids. This may also result in breakthrough bleeding.

Concurrent use of bosentan and ethinyl estradiol-containing products may result in decreased concentrations of these contraceptive hormones, thereby increasing the risk of unintended pregnancy and unscheduled bleeding.

Increase in plasma levels associated with co-administered drugs

Co-administration of atorvastatin and certain oral contraceptives containing ethinyl estradiol increase AUC values for ethinyl estradiol by approximately 20%. Ascorbic acid and acetaminophen may increase plasma ethinyl estradiol levels, possibly by inhibition of conjugation. CYP 3A4 inhibitors such as itraconazole or ketoconazole may increase plasma hormone levels.

Changes in plasma levels of co-administered drugs

Combination hormonal contraceptives containing some synthetic estrogens (e.g., ethinyl estradiol) may inhibit the metabolism of other compounds. Increased plasma concentrations of cyclosporine, prednisolone, and theophylline have been reported with concomitant administration of oral contraceptives. Decreased plasma concentrations of acetaminophen and increased clearance of temazepam, salicylic acid, morphine and clofibric acid, due to induction of conjugation, have been noted when these drugs were administered with oral contraceptives.

Combined hormonal contraceptives have been shown to significantly decrease plasma concentrations of lamotrigine when co-administered due to induction of lamotrigine glucuronidation. This may reduce seizure control; therefore, dosage adjustments of lamotrigine may be necessary.^101

Healthcare professionals are advised to also refer to prescribing information of co-administered drugs for recommendations regarding management of concomitant therapy.

9. Interactions with Laboratory Tests

Certain endocrine and liver function tests and blood components may be affected by oral contraceptives:

1. Increased prothrombin and factors VII, VIII, IX, and X; decreased antithrombin 3; increased norepinephrine-induced platelet aggregability.
2. Increased thyroid binding globulin (TBG) leading to increased circulating total thyroid hormone, as measured by protein-bound iodine (PBI), T4 by column or by radioimmunoassay. Free T3 resin uptake is decreased, reflecting the elevated TBG, free T4 concentration is unaltered.
3. Other binding proteins may be elevated in serum.
4. Sex hormone binding globulins are increased and result in elevated levels of total circulating sex steroids; however, free or biologically active levels either decrease or remain unchanged.
5. Triglycerides may be increased and levels of various other lipids and lipoproteins may be affected.
6. Glucose tolerance may be decreased.
7. Serum folate levels may be depressed by oral contraceptive therapy. This may be of clinical significance if a woman becomes pregnant shortly after discontinuing oral contraceptives.

10. Carcinogenesis

See WARNINGS.

11. Pregnancy

Pregnancy Category X

See CONTRAINDICATIONS and WARNINGS.

12. Nursing Mothers

Small amounts of oral contraceptive steroids have been identified in the milk of nursing mothers and a few adverse effects on the child have been reported, including jaundice and breast enlargement. In addition, combination oral contraceptives given in the postpartum period may interfere with lactation by decreasing the quantity and quality of breast milk. If possible, the nursing mother should be advised not to use combination oral contraceptives but to use other forms of contraception until she has completely weaned her child.

13. Pediatric Use

Safety and efficacy of TriNessa® has been established in women of reproductive age. Safety and efficacy are expected to be the same for postpubertal adolescents under the age of 16 and for users 16 years and older. There was no significant difference between TriNessa® Tablets and placebo in mean change in total lumbar spine (L1–L4) and total hip bone mineral density between baseline and Cycle 13 in 123 adolescent females with anorexia nervosa in a double-blind, placebo-controlled, multicenter, one-year treatment duration clinical trial for the Intent To Treat (ITT) population. Use of this product before menarche is not indicated.

14. Geriatric Use

This product has not been studied in women over 65 years of age and is not indicated in this population.

INFORMATION FOR THE PATIENT

See Patient Labeling printed below.

ADVERSE REACTIONS

An increased risk of the following serious adverse reactions has been associated with the use of oral contraceptives (see WARNINGS).

- Thrombophlebitis and venous thrombosis with or without embolism
- Arterial thromboembolism
- Pulmonary embolism
- Myocardial infarction
- Cerebral hemorrhage
- Cerebral thrombosis
- Hypertension
- Gallbladder disease
- Hepatic adenomas or benign liver tumors

There is evidence of an association between the following conditions and the use of oral contraceptives:

- Mesenteric thrombosis
- Retinal thrombosis

The following adverse reactions have been reported in patients receiving oral contraceptives and are believed to be drug-related:

- Nausea
- Vomiting
- Gastrointestinal symptoms (such as abdominal cramps and bloating)
- Breakthrough bleeding
- Spotting
- Change in menstrual flow
- Amenorrhea
- Temporary infertility after discontinuation of treatment
- Edema
- Melasma which may persist
- Breast changes: tenderness, enlargement, secretion
- Change in weight (increase or decrease)
- Change in cervical erosion and secretion
- Diminution in lactation when given immediately postpartum
- Cholestatic jaundice
- Migraine
- Allergic reaction, including rash, urticaria, angioedema
- Mental depression
- Reduced tolerance to carbohydrates
- Vaginal candidiasis
- Change in corneal curvature (steepening)
- Intolerance to contact lenses

The following adverse reactions have been reported in users of oral contraceptives and a causal association has been neither confirmed nor refuted:

- Pre-menstrual syndrome
- Cataracts
- Changes in appetite
- Cystitis-like syndrome
- Headache
- Nervousness
- Dizziness
- Hirsutism
- Loss of scalp hair
- Erythema multiforme
- Erythema nodosum
- Hemorrhagic eruption
- Vaginitis
- Porphyria
- Impaired renal function
- Hemolytic uremic syndrome
- Acne
- Changes in libido
- Colitis
- Budd-Chiari Syndrome

OVERDOSAGE

Serious ill effects have not been reported following acute ingestion of large doses of oral contraceptives by young children. Overdosage may cause nausea and withdrawal bleeding may occur in females.

NON-CONTRACEPTIVE HEALTH BENEFITS

The following non-contraceptive health benefits related to the use of combination oral contraceptives are supported by epidemiological studies which largely utilized oral contraceptive formulations containing estrogen doses exceeding 0.035 mg of ethinyl estradiol or 0.05 mg mestranol.^73–78

Effects on menses:

- increased menstrual cycle regularity
- decreased blood loss and decreased incidence of iron deficiency anemia
- decreased incidence of dysmenorrhea

Effects related to inhibition of ovulation:

- decreased incidence of functional ovarian cysts
- decreased incidence of ectopic pregnancies

Other effects:

- decreased incidence of fibroadenomas and fibrocystic disease of the breast
- decreased incidence of acute pelvic inflammatory disease
- decreased incidence of endometrial cancer
- decreased incidence of ovarian cancer

DOSAGE AND ADMINISTRATION

Oral Contraception

To achieve maximum contraceptive effectiveness, TriNessa® must be taken exactly as directed and at intervals not exceeding 24 hours. The possibility of ovulation and conception prior to initiation of medication should be considered. TriNessa® is available in a blister card with a tablet dispenser which is preset for a Sunday Start. Day 1 Start is also provided.

Sunday Start

When taking TriNessa® the first white tablet should be taken on the first Sunday after menstruation begins. If the period begins on Sunday, the first tablet should be taken that day. Take one active tablet daily for 21 days followed by one dark green inactive tablet daily for 7 days. After 28 tablets have been taken, a new course is started the next day (Sunday). For the first cycle of a Sunday Start regimen, another method of contraception should be used until after the first 7 consecutive days of administration.

If the patient misses one (1) active tablet in Weeks 1, 2, or 3, the tablet should be taken as soon as she remembers. If the patient misses two (2) active tablets in Week 1 or Week 2, the patient should take two (2) tablets the day she remembers and two (2) tablets the next day; and then continue taking one (1) tablet a day until she finishes the pack. The patient should be instructed to use a back-up method of birth control such as a condom or spermicide if she has sex in the seven (7) days after missing pills. If the patient misses two (2) active tablets in the third week or misses three (3) or more active tablets in a row, the patient should continue taking one tablet every day until Sunday. On Sunday the patient should throw out the rest of the pack and start a new pack that same day. The patient should be instructed to use a back-up method of birth control if she has sex in the seven (7) days after missing pills.

Complete instructions to facilitate patient counseling on proper pill usage may be found in the Detailed Patient Labeling ("How to Take the Pill" section).

Day 1 Start

The dosage of TriNessa® for the initial cycle of therapy is one active tablet administered daily from the 1st day through the 21st day of the menstrual cycle, counting the first day of menstrual flow as "Day 1" followed by one dark green inactive tablet daily for 7 days. Tablets are taken without interruption for 28 days. After 28 tablets have been taken, a new course is started the next day.

If the patient misses one (1) active tablet in Weeks 1, 2, or 3, the tablet should be taken as soon as she remembers. If the patient misses two (2) active tablets in Week 1 or Week 2, the patient should take two (2) tablets the day she remembers and two (2) tablets the next day; and then continue taking one (1) tablet a day until she finishes the pack. The patient should be instructed to use a back-up method of birth control such as a condom or spermicide if she has sex in the seven (7) days after missing pills. If the patient misses two (2) active tablets in the third week or misses three (3) or more active tablets in a row, the patient should throw out the rest of the pack and start a new pack that same day. The patient should be instructed to use a back-up method of birth control if she has sex in the seven (7) days after missing pills.

Complete instructions to facilitate patient counseling on proper pill usage may be found in the Detailed Patient Labeling ("How to Take the Pill" section).

The use of TriNessa® for contraception may be initiated 4 weeks postpartum in women who elect not to breastfeed. When the tablets are administered during the postpartum period, the increased risk of thromboembolic disease associated with the postpartum period must be considered. (See CONTRAINDICATIONS and WARNINGS concerning thromboembolic disease. See also PRECAUTIONS: Nursing Mothers.) The possibility of ovulation and conception prior to initiation of medication should be considered.

(See Discussion of Dose-Related Risk of Vascular Disease from Oral Contraceptives.)

ADDITIONAL INSTRUCTIONS

Breakthrough bleeding, spotting, and amenorrhea are frequent reasons for patients discontinuing oral contraceptives. In breakthrough bleeding, as in all cases of irregular bleeding from the vagina, nonfunctional causes should be borne in mind. In undiagnosed persistent or recurrent abnormal bleeding from the vagina, adequate diagnostic measures are indicated to rule out pregnancy or malignancy. If pathology has been excluded, time or a change to another formulation may solve the problem. Changing to an oral contraceptive with a higher estrogen content, while potentially useful in minimizing menstrual irregularity, should be done only if necessary since this may increase the risk of thromboembolic disease.

Use of oral contraceptives in the event of a missed menstrual period:

1. If the patient has not adhered to the prescribed schedule, the possibility of pregnancy should be considered at the time of the first missed period and oral contraceptive use should be discontinued if pregnancy is confirmed.
2. If the patient has adhered to the prescribed regimen and misses two consecutive periods, pregnancy should be ruled out.

ACNE

The timing of initiation of dosing with TriNessa® for acne should follow the guidelines for use of TriNessa® as an oral contraceptive. Consult the DOSAGE AND ADMINISTRATION section for oral contraceptives. The dosage regimen for TriNessa® for treatment of facial acne, as available in a blister card with a tablet dispenser, utilizes a 21-day active and a 7-day placebo schedule. Take one active tablet daily for 21 days followed by one dark green inactive tablet for 7 days. After 28 tablets have been taken, a new course is started the next day.

HOW SUPPLIED

TriNessa® is available in a blister card (NDC 54868-5826-0) with a tablet dispenser (unfilled). The blister card contains 28 tablets as follows: 7 white tablets, 7 light blue tablets, 7 blue tablets, and 7 dark green tablets. Each white tablet contains 0.180 mg of the progestational compound, norgestimate, together with 0.035 mg of the estrogenic compound, ethinyl estradiol. Each light blue tablet contains 0.215 mg of the progestational compound, norgestimate, together with 0.035 mg of the estrogenic compound, ethinyl estradiol. Each blue tablet contains 0.250 mg of the progestational compound, norgestimate, together with 0.035 mg of the estrogenic compound, ethinyl estradiol. Each dark green tablet contains inert ingredients.

0.180/0.035 mg tablets - White, round, biconvex, coated tablet imprinted "WPI" on one side and "524" on the other side of the tablet.

0.215/0.035 mg tablets - Light blue, round, biconvex, coated tablet imprinted "WPI" on one side and "525" on the other side of the tablet.

0.250/0.035 mg tablets - Blue, round, biconvex, coated tablet imprinted "WPI" on one side and "526" on the other side of the tablet.

Each dark green reminder pill is a round, biconvex, coated tablet imprinted "WPI" on one side and "P" on the other side.

Keep out of reach of children.

Store at 25°C (77°F); excursions permitted to 15° – 30°C (59° – 86°F).

Protect from light.

REFERENCES

1. Trussel J. Contraceptive efficacy. In Hatcher RA, Trussel J, Stewart F, Cates W, Stewart GK, Kowal D, Guest F, Contraceptive Technology: Seventeenth Revised Edition. New York NY: Irvington Publishers, 1998, in press.
2. Stadel BV, Oral contraceptives and cardiovascular disease. (Pt.1). N Engl J Med 1981; 305:612–618.
3. Stadel BV, Oral contraceptives and cardiovascular disease. (Pt.2). N Engl J Med 1981; 305:672–677.
4. Adam SA, Thorogood M. Oral contraception and myocardial infarction revisited: the effects of new preparations and prescribing patterns. Br J Obstet Gynaecol 1981; 88:838–845.
5. Mann Jl, Inman WH. Oral contraceptives and death from myocardial infarction. Br Med J 1975; 2(5965):245–248.
6. Mann Jl, Vessey MP, Thorogood M, Doll R. Myocardial infarction in young women with special reference to oral contraceptive practice. Br Med J 1975; 2(5956):241–245.
7. Royal College of General Practitioners' Oral Contraception Study: Further analyses of mortality in oral contraceptive users. Lancet 1981; 1:541–546.
8. Slone D, Shapiro S, Kaufman DW, Rosenberg L, Miettinen OS, Stolley PD. Risk of myocardial infarction in relation to current and discontinued use of oral contraceptives. N Engl J Med 1981:305:420–424.
9. Vessey MP. Female hormones and vascular disease-an epidemiological overview. Br J Fam Plann 1980; 6(Supplement): 1–12.
10. Russell-Briefel RG, Ezzati TM, Fulwood R, Perlman JA, Murphy RS. Cardiovascular risk status and oral contraceptive use, United States, 1976–80. Prevent Med 1986; 15:352–362.
11. Goldbaum GM, Kendrick JS, Hogelin GC, Gentry EM. The relative impact of smoking and oral contraceptive use on women in the United States. JAMA 1987; 258:1339–1342.
12. Layde PM, Beral V. Further analyses of mortality in oral contraceptive users; Royal College of General Practitioners' Oral Contraception Study. (Table 5) Lancet 1981; 1:541–546.
13. Knopp RH. Arteriosclerosis risk: the roles of oral contraceptives and postmenopausal estrogens. J Reprod Med 1986; 31(9) (Supplement):913–921.
14. Krauss RM, Roy S, Mishell DR, Casagrande J, Pike MC. Effects of two low-dose oral contraceptives on serum lipids and lipoproteins: Differential changes in high-density lipoproteins subclasses. Am J Obstet 1983; 145:446–452.
15. Wahl P, Walden C, Knopp R, Hoover J, Wallace R, Heiss G, Rifkind B. Effect of estrogen/progestin potency on lipid/lipoprotein cholesterol. N Engl J Med 1983; 308:862–867.
16. Wynn V, Niththyananthan R. The effect of progestin in combined oral contraceptives on serum lipids with special reference to high density lipoproteins. Am J Obstet Gynecol 1982;142:766–771.
17. Wynn V, Godsland I. Effects of oral contraceptives on carbohydrate metabolism. J Reprod Med 1986;31(9)(Supplement):892–897.
18. LaRosa JC. Atherosclerotic risk factors in cardiovascular disease. J Reprod Med 1986;31(9)(Supplement):906–912.
19. Inman WH, Vessey MP. Investigation of death from pulmonary, coronary, and cerebral thrombosis and embolism in women of child-bearing age. Br Med J 1968;2(5599):193–199.
20. Maguire MG, Tonascia J, Sartwell PE, Stolley PD, Tockman MS. Increased risk of thrombosis due to oral contraceptives: a further report. Am J Epidemiol 1979;110(2):188–195.
21. Petitti DB, Wingerd J, Pellegrin F, Ramacharan S. Risk of vascular disease in women: smoking, oral contraceptives, noncontraceptive estrogens, and other factors. JAMA 1979;242:1150–1154.
22. Vessey MP, Doll R, Investigation of relation between use of oral contraceptives and thromboembolic disease. Br Med J 1968;2(5599):199–205.
23. Vessey MP, Doll R. Investigation of relation between use of oral contraceptives and thromboembolic disease. A further report. Br Med J 1969; 2(5658):651–657.
24. Porter JB, Hunter JR, Danielson DA, Jick H, Stergachis A. Oral contraceptives and non-fatal vascular disease - recent experience. Obstet Gynecol 1982;59(3):299–302.
25. Vessey M, Doll R, Peto R, Johnson B, Wiggins P. A long-term follow-up study of women using different methods of contraception: an interim report. J Biosocial Sci 1976;8:375–427.
26. Royal College of General Practitioners: Oral Contraceptives, venous thrombosis, and varicose veins. J Royal Coll Gen Pract 1978; 28:393–399.
27. Collaborative Group for the Study of Stroke in Young Women: Oral contraception and increased risk of cerebral ischemia or thrombosis. N Engl J Med 1973;288:871–878.
28. Petitti DB, Wingerd J. Use of oral contraceptives, cigarette smoking, and risk of subarachnoid hemorrhage. Lancet 1978;2:234–236.
29. Inman WH. Oral contraceptives and fatal subarachnoid hemorrhage. Br Med J 1979:2(6203):1468–1470.
30. Collaborative Group for the Study of Stroke in Young Women: Oral Contraceptives and stroke in young women: associated risk factors. JAMA 1975; 231:718–722.
31. Inman WH, Vessey MP, Westerholm B, Engelund A. Thromboembolic disease and the steroidal content of oral contraceptives. A report to the Committee on Safety of Drugs. Br Med J 1970;2:203–209.
32. Meade TW, Greenberg G, Thompson SG. Progestogens and cardiovascular reactions associated with oral contraceptives and a comparison of the safety of 50- and 35-mcg oestrogen preparations. Br Med J 1980;280(6224):1157–1161.
33. Kay CR. Progestogens and arterial disease - evidence from the Royal College of General Practitioners' Study. Am J Obstet Gynecol 1982;142:762–765.
34. Royal College of General Practitioners: Incidence of arterial disease among oral contraceptive users. J Royal Coll Gen Pract 1983;33:75–82.
35. Ory HW. Mortality associated with fertility and fertility control: 1983. Family Planning Perspectives 1983;15:50–56.
36. The Cancer and Steroid Hormone Study of the Centers for Disease Control and the National Institute of Child Health and Human Development: Oral contraceptive use and the risk of breast cancer. N Engl J Med 1986;315:405–411.
37. Pike MC, Henderson BE, Krailo MD, Duke A, Roy S. Breast cancer in young women and use of oral contraceptives: possible modifying effect of formulation and age at use. Lancet 1983;2:926–929.
38. Paul C, Skegg DG, Spears GFS, Kaldor JM. Oral contraceptives and breast cancer: A national study. Br Med J 1986; 293:723–725.
39. Miller DR, Rosenberg L, Kaufman DW, Schottenfeld D, Stolley PD, Shapiro S. Breast cancer risk in relation to early oral contraceptive use. Obstet Gynecol 1986;68:863–868.
40. Olsson H, Olsson ML, Moller TR, Ranstam J, Holm P. Oral contraceptive use and breast cancer in young women in Sweden (letter). Lancet 1985; 1(8431):748–749.
41. McPherson K, Vessey M, Neil A, Doll R, Jones L, Roberts M. Early contraceptive use and breast cancer: Results of another case-control study. Br J Cancer 1987; 56:653–660.
42. Huggins GR, Zucker PF. Oral contraceptives and neoplasia: 1987 update. Fertil Steril 1987; 47:733–761.
43. McPherson K, Drife JO. The pill and breast cancer: why the uncertainty? Br Med J 1986; 293:709–710.
44. Shapiro S. Oral contraceptives - time to take stock. N Engl J Med 1987; 315:450–451.
45. Ory H, Naib Z, Conger SB, Hatcher RA, Tyler CW. Contraceptive choice and prevalence of cervical dysplasia and carcinoma in situ. Am J Obstet Gynecol 1976; 124:573–577.
46. Vessey MP, Lawless M, McPherson K, Yeates D. Neoplasia of the cervix uteri and contraception: a possible adverse effect of the pill. Lancet 1983; 2:930.
47. Brinton LA, Huggins GR, Lehman HF, Malli K, Savitz DA, Trapido E, Rosenthal J, Hoover R. Long term use of oral contraceptives and risk of invasive cervical cancer. Int J Cancer 1986; 38:339–344.
48. WHO Collaborative Study of Neoplasia and Steroid Contraceptives: Invasive cervical cancer and combined oral contraceptives. Br Med J 1985; 290:961–965.
49. Rooks JB, Ory HW, Ishak KG, Strauss LT, Greenspan JR, Hill AP, Tyler CW. Epidemiology of hepatocellular adenoma: the role of oral contraceptive use. JAMA 1979; 242:644–648.
50. Bein NN, Goldsmith HS. Recurrent massive hemorrhage from benign hepatic tumors secondary to oral contraceptives. Br J Surg 1977; 64:433–435.
51. Klatskin G. Hepatic tumors: possible relationship to use of oral contraceptives. Gastroenterology 1977; 73:386–394.
52. Henderson BE, Preston-Martin S, Edmondson HA, Peters RL, Pike MC. Hepatocellular carcinoma and oral contraceptives. Br J Cancer 1983;48:437–440.
53. Neuberger J, Forman D, Doll R, Williams R. Oral contraceptives and hepatocellular carcinoma. Br Med J 1986; 292:1355–1357.
54. Forman D, Vincent TJ, Doll R. Cancer of the liver and oral contraceptives. Br Med J 1986; 292:1357–1361.
55. Harlap S, Eldor J. Births following oral contraceptive failures. Obstet Gynecol 1980; 55:447–452.
56. Savolainen E, Saksela E, Saxen L. Teratogenic hazards of oral contraceptives analyzed in a national malformation register. Am J Obstet Gynecol 1981: 140:521–524.
57. Janerich DT, Piper JM, Glebatis DM. Oral contraceptives and birth defects. Am J Epidemiol 1980; 112:73–79.
58. Ferencz C, Matanoski GM, Wilson PD, Rubin JD, Neill CA, Gutberlet R. Maternal hormone therapy and congenital heart disease. Teratology 1980; 21:225–239.
59. Rothman KJ, Fyler DC, Goldblatt A, Kreidberg MB. Exogenous hormones and other drug exposures of children with congenital heart disease. Am J Epidemiol 1979; 109:433–439.
60. Boston Collaborative Drug Surveillance Program: Oral contraceptives and venous thromboembolic disease, surgically confirmed gallbladder disease, and breast tumors. Lancet 1973; 1:1399–1404.
61. Royal College of General Practitioners: Oral contraceptives and health. New York, Pittman 1974.
62. Layde PM, Vessey MP, Yeates D. Risk of gallbladder disease: a cohort study of young women attending family planning clinics. J Epidemiol Community Health 1982; 36:274–278.
63. Rome Group for Epidemiology and Prevention of Cholelithiasis (GREPCO): Prevalence of gallstone disease in an Italian adult female population. Am J Epidemiol 1984; 119:796–805.
64. Storm BL, Tamragouri RT, Morse ML, Lazar EL, West SL, Stolley PD, Jones JK. Oral contraceptives and other risk factors for gallbladder disease. Clin Pharmacol Ther 1986; 39:335–341.
65. Wynn V, Adams PW, Godsland IF, Melrose J, Niththyananthan R, Oakley NW, Seedj A. Comparison of effects of different combined oral contraceptive formulations on carbohydrate and lipid metabolism. Lancet 1979; 1:1045–1049.
66. Wynn V. Effect of progesterone and progestins on carbohydrate metabolism. In: Progesterone and Progestin. Bardin CW, Milgrom E, Mauvis-Jarvis P. eds. New York, Raven Press 1983; pp. 395–410.
67. Perlman JA, Roussell-Briefel RG, Ezzati TM, Lieberknecht G. Oral glucose tolerance and the potency of oral contraceptive progestogens. J Chronic Dis 1985;38:857–864.
68. Royal College of General Practitioners' Oral Contraception Study: Effect on hypertension and benign breast disease of progestogen component in combined oral contraceptives. Lancet 1977; 1:624.
69. Fisch IR, Frank J. Oral contraceptives and blood pressure. JAMA 1977; 237:2499–2503.
70. Laragh AJ. Oral contraceptive induced hypertension-nine years later. Am J Obstet Gynecol 1976; 126:141–147.
71. Ramcharan S, Peritz E, Pellegrin FA, Williams WT. Incidence of hypertension in the Walnut Creek Contraceptive Drug Study cohort: In: Pharmacology of steroid contraceptive drugs. Garattini S, Berendes HW. Eds. New York, Raven Press, 1977; pp. 277–288, (Monographs of the Mario Negri Institute for Pharmacological Research Milan.)
72. Stockley I. Interactions with oral contraceptives. J Pharm 1976;216:140–143.
73. The Cancer and Steroid Hormone Study of the Centers for Disease Control and the National Institute of Child Health and Human Development: Oral contraceptive use and the risk of ovarian cancer. JAMA 1983; 249:1596–1599.
74. The Cancer and Steroid Hormone Study of the Centers for Disease Control and the National Institute of Child Health and Human Development: Combination oral contraceptive use and the risk of endometrial cancer. JAMA 1987; 257:796–800.
75. Ory HW. Functional ovarian cysts and oral contraceptives: negative association confirmed surgically. JAMA 1974; 228:68–69.
76. Ory HW, Cole P, MacMahon B, Hoover R. Oral contraceptives and reduced risk of benign breast disease. N Engl J Med 1976; 294:419–422.
77. Ory HW. The noncontraceptive health benefits from oral contraceptive use. Fam Plann Perspect 1982; 14:182–184.
78. Ory HW, Forrest JD, Lincoln R. Making choices: Evaluating the health risks and benefits of birth control methods. New York, The Alan Guttmacher Institute, 1983; p.1.
79. Schlesselman J, Stadel BV, Murray P, Lai S. Breast cancer in relation to early use of oral contraceptives. JAMA 1988; 259:1828–1833.
80. Hennekens CH, Speizer FE, Lipnick RJ, Rosner B, Bain C, Belanger C, Stampfer MJ, Willett W, Peto R. A case-control study of oral contraceptive use and breast cancer. JNCI 1984; 72:39–42.
81. LaVecchia C, Decarli A, Fasoli M, Franceschi S, Gentile A, Negri E, Parazzini F, Tognoni G. Oral contraceptives and cancers of the breast and of the female genital tract. Interim results from a case-control study. Br J Cancer 1986; 54:311–317.
82. Meirik O, Lund E, Adami H, Bergstrom R, Christoffersen T, Bergsjo P. Oral contraceptive use and breast cancer in young women. A Joint National Case-control study in Sweden and Norway. Lancet 1986; 11:650–654.
83. Kay CR, Hannaford PC. Breast cancer and the pill-A further report from the Royal College of General Practitioners' oral contraception study. Br J Cancer 1988;58:675–680.
84. Stadel BV, Lai S, Schlesselman JJ, Murray P. Oral contraceptives and premenopausal breast cancer in nulliparous women. Contraception 1988; 38:287–299.
85. Miller DR, Rosenberg L, Kaufman DW, Stolley P, Warshauer ME, Shapiro S. Breast cancer before age 45 and oral contraceptive use: New Findings. Am J Epidemiol 1989; 129:269–280.
86. The UK National Case–Control Study Group, Oral contraceptive use and breast cancer risk in young women. Lancet 1989; 1:973–982.
87. Schlesselman JJ. Cancer of the breast and reproductive tract in relation to use of oral contraceptives. Contraception 1989; 40:1–38.
88. Vessey MP, McPherson K, Villard-Mackintosh L, Yeates D. Oral contraceptives and breast cancer: latest findings in a large cohort study. Br J Cancer 1989; 59:613–617.
89. Jick SS, Walker AM, Stergachis A, Jick H. Oral contraceptives and breast cancer. Br J Cancer 1989; 59:618–621.
90. Anderson FD, Selectivity and minimal androgenicity of norgestimate in monophasic and triphasic oral contraceptives. Acta Obstet Gynecol Scand 1992; 156 (Supplement):15–21.
91. Chapdelaine A, Desmaris J-L, Derman RJ. Clinical evidence of minimal androgenic activity of norgestimate. Int J Fertil 1989; 34(51):347–352.
92. Phillips A, Demarest K, Hahn DW, Wong F, McGuire JL. Progestational and androgenic receptor binding affinities and in vivo activities of norgestimate and other progestins. Contraception 1989; 41(4):399–409.
93. Phillips A, Hahn DW, Klimek S, McGuire JL. A comparison of the potencies and activities of progestogens used in contraceptives. Contraception 1987; 36(2):181–192.
94. Janaud A, Rouffy J, Upmalis D, Dain M-P. A comparison study of lipid and androgen metabolism with triphasic oral contraceptive formulations containing norgestimate or levonorgestrel. Acta Obstet Gynecol Scand 1992; 156 (Supplement):34–38.
95. Collaborative Group on Hormonal Factors in Breast Cancer. Breast cancer and hormonal contraceptives: collaborative reanalysis of individual data on 53,297 women with breast cancer and 100,239 women without breast cancer from 54 epidemiological studies. Lancet 1996; 347:1713–1727.
96. Palmer JR, Rosenberg L, Kaufman DW, Warshauer ME, Stolley P, Shapiro S. Oral Contraceptive Use and Liver Cancer. Am J Epidemiol 1989;130:878–882.
97. Lewis M, Spitzer WO, Heinemann LAJ, MacRae KD, Bruppacher R, Thorogood M on behalf of Transnational Research Group on Oral Contraceptives and Health of Young Women. Third generation oral contraceptives and risk of myocardial infarction: an international case-control study. Br Med J, 1996;312:88–90.
98. Improving access to quality care in family planning: Medical eligibility criteria for contraceptive use. Geneva, WHO, Family and Reproductive Health, 1996.
99. Bork K, Fischer B, DeWald G. Recurrent episodes of skin angioedema and severe attacks of abdominal pain induced by oral contraceptives or hormone replacement therapy. Am J Med 2003;114:294–298.
100. Van Giersbergen PLM, Halabi A, Dingemanse J. Pharmacokinetic interaction between bosentan and the oral contraceptives norethisterone and ethinyl estradiol. Int J Clin Pharmacol Ther 2006;44(3):113–118.
101. Christensen J, Petrenaite V, Atterman J, et al. Oral contraceptives induce lamotrigine metabolism: evidence from a double-blind, placebo-controlled trial. Epilepsia 2007;48(3):484–489.

BRIEF SUMMARY PATIENT PACKAGE INSERT

This product (like all oral contraceptives) does not protect against HIV infection (AIDS) and other sexually transmitted diseases.

Oral contraceptives, also known as "birth control pills" or "the pill," are taken to prevent pregnancy. When taken correctly to prevent pregnancy, oral contraceptives have a failure rate of approximately 1% per year (1 pregnancy per 100 women per year of use) when used without missing any pills. The typical failure rate is approximately 5% per year (5 pregnancies per 100 women per year of use) when women who miss pills are included. For most women oral contraceptives are also free of serious or unpleasant side effects. However, forgetting to take pills considerably increases the chances of pregnancy.

TriNessa® may also be taken to treat moderate acne in females at least 15 years of age, who have started having menstrual periods, are able to take the pill and want to use the pill for birth control.

For the majority of women, oral contraceptives can be taken safely. But there are some women who are at high risk of developing certain serious diseases that can be fatal or may cause temporary or permanent disability. The risks associated with taking oral contraceptives increase significantly if you:

- smoke
- have high blood pressure, diabetes, high cholesterol
- have or have had clotting disorders, heart attack, stroke, angina pectoris, cancer of the breast or sex organs, jaundice or malignant or benign liver tumors.

Although cardiovascular disease risks may be increased with oral contraceptive use after age 40 in healthy, non-smoking women (even with the newer low-dose formulations), there are also greater potential health risks associated with pregnancy in older women.

You should not take the pill if you suspect you are pregnant or have unexplained vaginal bleeding.

BOXED WARNING

Cigarette smoking increases the risk of serious cardiovascular side effects from oral contraceptive use. This risk increases with age and with heavy smoking (15 or more cigarettes per day) and is quite marked in women over 35 years of age. Women who use oral contraceptives are strongly advised not to smoke.

Most side effects of the pill are not serious. The most common side effects are nausea, vomiting, bleeding between menstrual periods, weight gain, breast tenderness, and difficulty wearing contact lenses. These side effects, especially nausea and vomiting, may subside within the first three months of use.

The serious side effects of the pill occur very infrequently, especially if you are in good health and are young. However, you should know that the following medical conditions have been associated with or made worse by the pill:

1. Blood clots in the legs (thrombophlebitis), lungs (pulmonary embolism), stoppage or rupture of a blood vessel in the brain (stroke), blockage of blood vessels in the heart (heart attack or angina pectoris) or other organs of the body. As mentioned above, smoking increases the risk of heart attacks and strokes and subsequent serious medical consequences.
2. In rare cases, oral contraceptives can cause benign but dangerous liver tumors. These benign liver tumors can rupture and cause fatal internal bleeding. In addition, some studies report an increased risk of developing liver cancer. However, liver cancers are rare.
3. High blood pressure, although blood pressure usually returns to normal when the pill is stopped.

The symptoms associated with these serious side effects are discussed in the detailed leaflet given to you with your supply of pills. Notify your healthcare professional if you notice any unusual physical disturbances while taking the pill. In addition, drugs such as rifampin, as well as some anticonvulsants and some antibiotics may decrease oral contraceptive effectiveness.

Oral contraceptives may interact with lamotrigine (LAMICTAL®), an anticonvulsant used for epilepsy. This may increase the risk of seizures so your healthcare professional may need to adjust the dose of lamotrigine.

Various studies give conflicting reports on the relationship between breast cancer and oral contraceptive use. Oral contraceptive use may slightly increase your chance of having breast cancer diagnosed, particularly after using hormonal contraceptives at a younger age. After you stop using hormonal contraceptives, the chances of having breast cancer diagnosed begin to go back down. You should have regular breast examinations by a healthcare professional and examine your own breasts monthly. Tell your healthcare professional if you have a family history of breast cancer or if you have had breast nodules or an abnormal mammogram. Women who currently have or have had breast cancer should not use oral contraceptives because breast cancer is usually a hormone-sensitive tumor.

Some studies have found an increase in the incidence of cancer of the cervix in women who use oral contraceptives. However, this finding may be related to factors other than the use of oral contraceptives. There is insufficient evidence to rule out the possibility that the pill may cause such cancers.

Taking the combination pill provides some important non-contraceptive benefits. These include less painful menstruation, less menstrual blood loss and anemia, fewer pelvic infections, and fewer cancers of the ovary and the lining of the uterus.

Be sure to discuss any medical condition you may have with your healthcare professional. Your healthcare professional will take a medical and family history before prescribing oral contraceptives and will examine you. The physical examination may be delayed to another time if you request it and the healthcare professional believes that it is a good medical practice to postpone it. You should be reexamined at least once a year while taking oral contraceptives. Your pharmacist should have given you the detailed patient information labeling which gives you further information which you should read and discuss with your healthcare professional.

HOW TO TAKE THE PILL

IMPORTANT POINTS TO REMEMBER

BEFORE YOU START TAKING YOUR PILLS:

1. BE SURE TO READ THESE DIRECTIONS:
  Before you start taking your pills.
  Anytime you are not sure what to do.
2. THE RIGHT WAY TO TAKE THE PILL IS TO TAKE ONE PILL EVERY DAY AT THE SAME TIME.
  If you miss pills you could get pregnant. This includes starting the pack late.
  The more pills you miss, the more likely you are to get pregnant.
3. MANY WOMEN HAVE SPOTTING OR LIGHT BLEEDING, OR MAY FEEL SICK TO THEIR STOMACH DURING THE FIRST 1–3 PACKS OF PILLS. If you feel sick to your stomach or have spotting or light bleeding, do not stop taking the pill. The problem will usually go away. If it doesn't go away, check with your healthcare professional.
4. MISSING PILLS CAN ALSO CAUSE SPOTTING OR LIGHT BLEEDING, even when you make up these missed pills.
  On the days you take 2 pills to make up for missed pills, you could also feel a little sick to your stomach.
5. IF YOU HAVE VOMITING OR DIARRHEA, OR IF YOU TAKE SOME MEDICINES, including some antibiotics, your pills may not work as well.
  Use a back-up method (such as a condom or spermicide) until you check with your healthcare professional.
6. IF YOU HAVE TROUBLE REMEMBERING TO TAKE THE PILL, talk to your healthcare professional about how to make pill-taking easier or about using another method of birth control.
7. IF YOU HAVE ANY QUESTIONS OR ARE UNSURE ABOUT THE INFORMATION IN THIS LEAFLET, call your healthcare professional.

BEFORE YOU START TAKING YOUR PILLS

1. DECIDE WHAT TIME OF DAY YOU WANT TO TAKE YOUR PILL.
  It is important to take it at about the same time every day.
2. LOOK AT YOUR PILL PACK
  The pill pack has 21 "active" pills (with hormones) to take for 3 weeks. This is followed by 1 week of "reminder" dark green pills (without hormones).
  There are 7 white "active" pills, 7 light blue "active" pills, 7 blue "active" pills, and 7 dark green "reminder" pills.
3. ALSO FIND:
  1) where on the pack to start taking pills,
  2) in what order to take the pills.
4. BE SURE YOU HAVE READY AT ALL TIMES:
  ANOTHER KIND OF BIRTH CONTROL (such as a condom or spermicide) to use as a back-up method in case you miss pills.
  AN EXTRA, FULL PILL PACK.

WHEN TO START THE FIRST PACK OF PILLS

You have a choice of which day to start taking your first pack of pills. TriNessa® is available in a blister card with a tablet dispenser which is preset for a Sunday Start. Day 1 Start is also provided. Decide with your healthcare professional which is the best day for you. Pick a time of day that will be easy to remember.

Sunday Start:

Take the first white "active" pill of the first pack on the Sunday after your period starts, even if you are still bleeding. If your period begins on Sunday, start the pack that same day.

Use another method of birth control such as a condom or spermicide as a back-up method if you have sex anytime from the Sunday you start your first pack until the next Sunday (7 days).

Day 1 Start:

Take the first white "active" pill of the first pack during the first 24 hours of your period.

You will not need to use a back-up method of birth control, since you are starting the pill at the beginning of your period.

WHAT TO DO DURING THE MONTH

1. TAKE ONE PILL AT THE SAME TIME EVERY DAY UNTIL THE PACK IS EMPTY.
  Do not skip pills even if you are spotting or bleeding between monthly periods or feel sick to your stomach (nausea).
  Do not skip pills even if you do not have sex very often.
2. WHEN YOU FINISH A PACK OR SWITCH YOUR BRAND OF PILLS:
  Start the next pack on the day after your last "reminder" pill. Do not wait any days between packs.

WHAT TO DO IF YOU MISS PILLS

If you MISS 1 white, light blue, or blue "active" pill:

1. Take it as soon as you remember. Take the next pill at your regular time. This means you may take 2 pills in 1 day.
2. You do not need to use a back-up birth control method if you have sex.

If you MISS 2 white or light blue "active" pills in a row in WEEK 1 OR WEEK 2 of your pack:

1. Take 2 pills on the day you remember and 2 pills the next day.
2. Then take 1 pill a day until you finish the pack.
3. You COULD BECOME PREGNANT if you have sex in the 7 days after you miss pills. You MUST use another birth control method (such as a condom or spermicide) as a back-up method for those 7 days.

If you MISS 2 blue "active" pills in a row in THE 3RD WEEK:

1. If you are a Sunday Starter:
  Keep taking 1 pill every day until Sunday. On Sunday, THROW OUT the rest of the pack and start a new pack of pills that same day.
  If you are a Day 1 Starter:
  THROW OUT the rest of the pill pack and start a new pack that same day.
2. You may not have your period this month but this is expected. However, if you miss your period 2 months in a row, call your healthcare professional because you might be pregnant.
3. You COULD BECOME PREGNANT if you have sex in the 7 days after you miss pills. You MUST use another birth control method (such as a condom or spermicide) as a back-up method for those 7 days.

If you MISS 3 OR MORE white, light blue, or blue "active" pills in a row (during the first 3 weeks):

1. If you are a Sunday Starter:
  Keep taking 1 pill every day until Sunday. On Sunday, THROW OUT the rest of the pack and start a new pack of pills that same day.
  If you are a Day 1 Starter:
  THROW OUT the rest of the pill pack and start a new pack that same day.
2. You may not have your period this month but this is expected. However, if you miss your period 2 months in a row, call your healthcare professional because you might be pregnant.
3. You COULD BECOME PREGNANT if you have sex in the 7 days after you miss pills. You MUST use another birth control method (such as a condom or spermicide) as a back-up method for those 7 days.

A REMINDER:

If you forget any of the 7 dark green "reminder" pills in WEEK 4:

THROW AWAY the pills you missed.

Keep taking 1 pill each day until the pack is empty.

You do not need a back-up method.

FINALLY, IF YOU ARE STILL NOT SURE WHAT TO DO ABOUT THE PILLS YOU HAVE MISSED:

Use a BACK-UP METHOD anytime you have sex.

KEEP TAKING ONE "ACTIVE" PILL EACH DAY until you can reach your healthcare professional.

INSTRUCTIONS FOR USE

1. Open the compact. Place the blister into the compact, with the tablets facing up, so that the V notch in the blister card matches up with the V-shaped post at the top of the compact. Press down firmly on each edge of the blister card and make sure that the edge of the card is firmly seated under each of the nibs inside the compact (see picture).
  There are 7 white "active" pills, 7 light blue "active" pills, 7 blue "active" pills and 7 dark green "reminder" pills.
2. If you are to start pill taking on Sunday, take your first white pill on the first Sunday after your menstrual period begins. If your period begins on Sunday, take your first pill that day. Remove the first pill at the top of the dispenser (Sunday) by pressing the pill through the hole in the bottom of the dispenser.
3. If you are to start pill taking on a day other than Sunday, the enclosed calendar label has been provided and will be placed over the calendar in the center of the blister card. To put the label in place, identify your correct starting day, locate that day printed in blue on the label, and line your blue starting day up with the first white pill which is directly under the V notch at the top of the dispenser. Remove the label from the backing. Press the center of the label down onto the center of the printed calendar. Remove that white pill by pressing the pill through the hole in the bottom of the dispenser.
4. Continue taking one pill daily, clockwise, until no pills remain in the outer ring.
5. The next day take the dark green pill from the inner ring that corresponds with the day of the week it happens to be. Take a dark green pill each day until all seven pills are taken. During this time your period should begin.
6. After you have taken all the dark green pills, begin a new blister card (see Step 1 above in "Instructions for Use") and take the first white "active" pill on the next day, even if your period is not yet over.

DETAILED PATIENT LABELING

PLEASE NOTE: This labeling is revised from time to time as important new medical information becomes available. Therefore, please review this labeling carefully.

This product (like all oral contraceptives) does not protect against HIV infection (AIDS) and other sexually transmitted diseases.

TriNessa® Regimen

Each white tablet contains 0.180 mg norgestimate and 0.035 mg ethinyl estradiol. Each light blue tablet contains 0.215 mg norgestimate and 0.035 mg ethinyl estradiol. Each blue tablet contains 0.250 mg norgestimate and 0.035 mg ethinyl estradiol. Each dark green tablet contains inert ingredients.

INTRODUCTION

Any woman who considers using oral contraceptives (the birth control pill or the pill) should understand the benefits and risks of using this form of birth control. This patient labeling will give you much of the information you will need to make this decision and will also help you determine if you are at risk of developing any of the serious side effects of the pill. It will tell you how to use the pill properly so that it will be as effective as possible. However, this labeling is not a replacement for a careful discussion between you and your healthcare professional. You should discuss the information provided in this labeling with him or her, both when you first start taking the pill and during your revisits. You should also follow your healthcare professional's advice with regard to regular check-ups while you are on the pill.

EFFECTIVENESS OF ORAL CONTRACEPTIVES FOR CONTRACEPTION

Oral contraceptives or "birth control pills" or "the pill" are used to prevent pregnancy and are more effective than most other non-surgical methods of birth control. When they are taken correctly without missing any pills, the chance of becoming pregnant is approximately 1% (1 pregnancy per 100 women per year of use). Typical failure rates, including women who do not always take the pill correctly, are approximately 5% per year (5 pregnancies per 100 women per year of use). The chance of becoming pregnant increases with each missed pill during a menstrual cycle.

In comparison, typical failure rates for other non-surgical methods of birth control during the first year of use are as follows:

Implant: <1% | Male sterilization: <1%
Injection: <1% | Cervical Cap with spermicides: 20 to 40%
IUD: 1 to 2% | Condom alone (male): 14%
Diaphragm with spermicides: 20% | Condom alone (female): 21%
Spermicides alone: 26% | Periodic abstinence: 25%
Vaginal sponge: 20 to 40% | Withdrawal: 19%
Female sterilization: <1% | No methods: 85%

TriNessa® may also be taken to treat moderate acne if all of the following are true:

- You have started having menstrual cycles
- You are at least 15 years old
- Your healthcare professional says it is safe for you to use the pill
- You want to use the pill for birth control

WHO SHOULD NOT TAKE ORAL CONTRACEPTIVES

BOXED WARNING

Cigarette smoking increases the risk of serious cardiovascular side effects from oral contraceptive use. This risk increases with age and with heavy smoking (15 or more cigarettes per day) and is quite marked in women over 35 years of age. Women who use oral contraceptives are strongly advised not to smoke.

Some women should not use the pill. For example, you should not take the pill if you have any of the following conditions:

- A history of heart attack or stroke
- Blood clots in the legs (thrombophlebitis), lungs (pulmonary embolism), or eyes
- A history of blood clots in the deep veins of your legs
- Chest pain (angina pectoris)
- Known or suspected breast cancer or cancer of the lining of the uterus, cervix or vagina
- Unexplained vaginal bleeding (until a diagnosis is reached by your healthcare professional)
- Yellowing of the whites of the eyes or of the skin (jaundice) during pregnancy or during previous use of the pill
- Liver tumor (benign or cancerous) or active liver disease
- Known or suspected pregnancy
- Valvular heart disease with complications
- Severe hypertension
- Diabetes with vascular involvement
- Headaches with focal neurological symptoms
- Major surgery with prolonged immobilization
- Hypersensitivity to any component of this product

Tell your healthcare professional if you have had any of these conditions. Your healthcare professional can recommend a safer method of birth control.

OTHER CONSIDERATIONS BEFORE TAKING ORAL CONTRACEPTIVES

Tell your healthcare professional if you have or have had:

- Breast nodules, fibrocystic disease of the breast, an abnormal breast x-ray or mammogram
- Diabetes
- Elevated cholesterol or triglycerides
- High blood pressure
- Migraine or other headaches or epilepsy
- Mental depression
- Gallbladder, liver, heart or kidney disease
- History of scanty or irregular menstrual periods

Women with any of these conditions should be checked often by their healthcare professional if they choose to use oral contraceptives.

Also, be sure to inform your healthcare professional if you smoke or are on any medications.

RISKS OF TAKING ORAL CONTRACEPTIVES

1. Risk of Developing Blood Clots

Blood clots and blockage of blood vessels are one of the most serious side effects of taking oral contraceptives and can cause death or serious disability. In particular, a clot in the legs can cause thrombophlebitis and a clot that travels to the lungs can cause a sudden blocking of the vessel carrying blood to the lungs. Rarely, clots occur in the blood vessels of the eye and may cause blindness, double vision, or impaired vision.

If you take oral contraceptives and need elective surgery, need to stay in bed for a prolonged illness or injury or have recently delivered a baby, you may be at risk of developing blood clots. You should consult your healthcare professional about stopping oral contraceptives four weeks before surgery and not taking oral contraceptives for two weeks after surgery or during bed rest. You should also not take oral contraceptives soon after delivery of a baby. It is advisable to wait for at least four weeks after delivery if you are not breastfeeding. If you are breastfeeding, you should wait until you have weaned your child before using the pill. (See also the section on Breastfeeding in General Precautions.)

The risk of circulatory disease in oral contraceptive users may be higher in users of high-dose pills and may be greater with longer duration of oral contraceptive use. In addition, some of these increased risks may continue for a number of years after stopping oral contraceptives. The risk of abnormal blood clotting increases with age in both users and nonusers of oral contraceptives, but the increased risk from the oral contraceptive appears to be present at all ages. For women aged 20 to 44 it is estimated that about 1 in 2,000 using oral contraceptives will be hospitalized each year because of abnormal clotting. Among nonusers in the same age group, about 1 in 20,000 would be hospitalized each year. For oral contraceptive users in general, it has been estimated that in women between the ages of 15 and 34 the risk of death due to a circulatory disorder is about 1 in 12,000 per year, whereas for nonusers the rate is about 1 in 50,000 per year. In the age group 35 to 44, the risk is estimated to be about 1 in 2,500 per year for oral contraceptive users and about 1 in 10,000 per year for nonusers.

2. Heart Attacks and Strokes

Oral contraceptives may increase the tendency to develop strokes (stoppage or rupture of blood vessels in the brain) and angina pectoris and heart attacks (blockage of blood vessels in the heart). Any of these conditions can cause death or serious disability.

Smoking greatly increases the possibility of suffering heart attacks and strokes. Furthermore, smoking and the use of oral contraceptives greatly increase the chances of developing and dying of heart disease.

3. Gallbladder Disease

Oral contraceptive users probably have a greater risk than nonusers of having gallbladder disease, although this risk may be related to pills containing high doses of estrogens.

4. Liver Tumors

In rare cases, oral contraceptives can cause benign but dangerous liver tumors. These benign liver tumors can rupture and cause fatal internal bleeding. In addition, some studies report an increased risk of developing liver cancer. However, liver cancers are rare.

5. Cancer of the Reproductive Organs and Breasts

Various studies give conflicting reports on the relationship between breast cancer and oral contraceptive use. Oral contraceptive use may slightly increase your chance of having breast cancer diagnosed, particularly after using hormonal contraceptives at a younger age. After you stop using hormonal contraceptives, the chances of having breast cancer diagnosed begin to go back down. You should have regular breast examinations by a healthcare professional and examine your own breasts monthly. Tell your healthcare professional if you have a family history of breast cancer or if you have had breast nodules or an abnormal mammogram. Women who currently have or have had breast cancer should not use oral contraceptives because breast cancer is usually a hormone-sensitive tumor.

Some studies have found an increase in the incidence of cancer of the cervix in women who use oral contraceptives. However, this finding may be related to factors other than the use of oral contraceptives. There is insufficient evidence to rule out the possibility that the pill may cause such cancers.

ESTIMATED RISK OF DEATH FROM A BIRTH CONTROL METHOD OR PREGNANCY

All methods of birth control and pregnancy are associated with a risk of developing certain diseases which may lead to disability or death. An estimate of the number of deaths associated with different methods of birth control and pregnancy has been calculated and is shown in the following table.

Annual Number of Birth-Related or Method-Related Deaths Associated with Control of Fertility per 100,000 Nonsterile Women, by Fertility Control Method According to Age
Method of control and outcome | 15–19 | 20–24 | 25–29 | 30–34 | 35–39 | 40–44
No fertility control methods [Deaths are birth-related] | 7.0 | 7.4 | 9.1 | 14.8 | 25.7 | 28.2
Oral contraceptives non-smoker [Deaths are method-related] | 0.3 | 0.5 | 0.9 | 1.9 | 13.8 | 31.6
Oral contraceptives smoker | 2.2 | 3.4 | 6.6 | 13.5 | 51.1 | 117.2
IUD | 0.8 | 0.8 | 1.0 | 1.0 | 1.4 | 1.4
Condom | 1.1 | 1.6 | 0.7 | 0.2 | 0.3 | 0.4
Diaphragm/spermicide | 1.9 | 1.2 | 1.2 | 1.3 | 2.2 | 2.8
Periodic abstinence | 2.5 | 1.6 | 1.6 | 1.7 | 2.9 | 3.6
Adapted from H.W. Ory, ref. #35.

In the above table, the risk of death from any birth control method is less than the risk of childbirth, except for oral contraceptive users over the age of 35 who smoke and pill users over the age of 40 even if they do not smoke. It can be seen in the table that for women aged 15 to 39, the risk of death was highest with pregnancy (7 to 26 deaths per 100,000 women, depending on age). Among pill users who do not smoke, the risk of death was always lower than that associated with pregnancy for any age group less than 40. Over the age of 40, the risk increases to 32 deaths per 100,000 women, compared to 28 associated with pregnancy in that age group. However, for pill users who smoke and are over the age of 35, the estimated number of deaths exceeds those for other methods of birth control. If a woman is over the age of 40 and smokes, her estimated risk of death is four times higher (117/100,000 women) than the estimated risk associated with pregnancy (28/100,000 women) in that age group.

The suggestion that women over 40 who do not smoke should not take oral contraceptives is based on information from older, higher-dose pills. An Advisory Committee of the FDA discussed this issue in 1989 and recommended that the benefits of low-dose oral contraceptive use by healthy, non-smoking women over 40 years of age may outweigh the possible risks. Older women, as all women, who take oral contraceptives, should take an oral contraceptive which contains the least amount of estrogen and progestogen that is compatible with the individual patient needs.

WARNING SIGNALS

If any of these adverse effects occur while you are taking oral contraceptives, call your healthcare professional immediately:

- Sharp chest pain, coughing of blood, or sudden shortness of breath (indicating a possible clot in the lung)
- Pain in the calf (indicating a possible clot in the leg)
- Crushing chest pain or heaviness in the chest (indicating a possible heart attack)
- Sudden severe headache or vomiting, dizziness or fainting, disturbances of vision or speech, weakness, or numbness in an arm or leg (indicating a possible stroke)
- Sudden partial or complete loss of vision (indicating a possible clot in the eye)
- Breast lumps (indicating possible breast cancer or fibrocystic disease of the breast; ask your healthcare professional to show you how to examine your breasts)
- Severe pain or tenderness in the stomach area (indicating a possibly ruptured liver tumor)
- Difficulty in sleeping, weakness, lack of energy, fatigue, or change in mood (possibly indicating severe depression)
- Jaundice or a yellowing of the skin or eyeballs, accompanied frequently by fever, fatigue, loss of appetite, dark colored urine, or light colored bowel movements (indicating possible liver problems)

SIDE EFFECTS OF ORAL CONTRACEPTIVES

In addition to the risks and more serious side effects discussed above, the following may also occur:

1. Irregular Vaginal Bleeding

Irregular vaginal bleeding or spotting may occur while you are taking the pills. Irregular bleeding may vary from slight staining between menstrual periods to breakthrough bleeding which is a flow much like a regular period. Irregular bleeding occurs most often during the first few months of oral contraceptive use, but may also occur after you have been taking the pill for some time. Such bleeding may be temporary and usually does not indicate any serious problems. It is important to continue taking your pills on schedule. If the bleeding occurs in more than one cycle or lasts for more than a few days, talk to your healthcare professional.

2. Contact Lenses

If you wear contact lenses and notice a change in vision or an inability to wear your lenses, contact your healthcare professional.

3. Fluid Retention

Oral contraceptives may cause edema (fluid retention) with swelling of the fingers or ankles and may raise your blood pressure. If you experience fluid retention, contact your healthcare professional.

4. Melasma

A spotty darkening of the skin is possible, particularly of the face, which may persist.

5. Other Side Effects

Other side effects may include nausea and vomiting, change in appetite, headache, nervousness, depression, dizziness, loss of scalp hair, rash, vaginal infections, and allergic reactions.

If any of these side effects bother you, call your healthcare professional.

GENERAL PRECAUTIONS

1. Missed Periods and Use of Oral Contraceptives Before or During Early Pregnancy

There may be times when you may not menstruate regularly after you have completed taking a cycle of pills. If you have taken your pills regularly and miss one menstrual period, continue taking your pills for the next cycle but be sure to inform your healthcare professional. If you have not taken the pills daily as instructed and missed a menstrual period, or if you missed two consecutive menstrual periods, you may be pregnant. Check with your healthcare professional immediately to determine whether you are pregnant. Stop taking your pills if you are pregnant.

There is no conclusive evidence that oral contraceptive use is associated with an increase in birth defects, when taken inadvertently during early pregnancy. Previously, a few studies had reported that oral contraceptives might be associated with birth defects, but these findings have not been seen in more recent studies. Nevertheless, oral contraceptives should not be used during pregnancy. You should check with your healthcare professional about risks to your unborn child of any medication taken during pregnancy.

2. While Breastfeeding

If you are breastfeeding, consult your healthcare professional before starting oral contraceptives. Some of the drug will be passed on to the child in the milk. A few adverse effects on the child have been reported, including yellowing of the skin (jaundice) and breast enlargement. In addition, combination oral contraceptives may decrease the amount and quality of your milk. If possible, do not use combination oral contraceptives while breastfeeding. You should use another method of contraception since breastfeeding provides only partial protection from becoming pregnant and this partial protection decreases significantly as you breastfeed for longer periods of time. You should consider starting combination oral contraceptives only after you have weaned your child completely.

3. Laboratory Tests

If you are scheduled for any laboratory tests, tell your healthcare professional you are taking birth control pills. Certain blood tests may be affected by birth control pills.

4. Drug Interactions

Certain drugs may interact with birth control pills to make them less effective in preventing pregnancy or cause an increase in breakthrough bleeding. Such drugs include rifampin, drugs used for epilepsy such as barbiturates (for example, phenobarbital), topiramate (Topamax®), carbamazepine (Tegretol® is one brand of this drug), or phenytoin (Dilantin® is one brand of this drug), phenylbutazone (Butazolidin® is one brand), certain drugs used in the treatment of HIV or AIDS, and possibly certain antibiotics. Medicine for pulmonary hypertension, such as bosentan (Tracleer®). Pregnancies and breakthrough bleeding have been reported by women who also used some form of the herbal supplement St. John's Wort while using combined hormonal contraceptives. Hormonal contraceptives may interact with lamotrigine (LAMICTAL®), an anticonvulsant used for epilepsy. This may increase the risk of seizures so your healthcare professional may need to adjust the dose of lamotrigine. You may need to use additional contraception when you take drugs which can make oral contraceptives less effective. Be sure to tell your healthcare professional if you are taking or start taking any medications while taking birth control pills.

5. Sexually Transmitted Diseases

TriNessa® (like all oral contraceptives) is intended to prevent pregnancy. Oral contraceptives do not protect against transmission of HIV (AIDS) and other sexually transmitted diseases such as chlamydia, genital herpes, genital warts, gonorrhea, hepatitis B, and syphilis.

HOW TO TAKE THE PILL

IMPORTANT POINTS TO REMEMBER

BEFORE YOU START TAKING YOUR PILLS:

1. BE SURE TO READ THESE DIRECTIONS:
  Before you start taking your pills.
  Anytime you are not sure what to do.
2. THE RIGHT WAY TO TAKE THE PILL IS TO TAKE ONE PILL EVERY DAY AT THE SAME TIME.
  If you miss pills you could get pregnant. This includes starting the pack late.
  The more pills you miss, the more likely you are to get pregnant.
3. MANY WOMEN HAVE SPOTTING OR LIGHT BLEEDING, OR MAY FEEL SICK TO THEIR STOMACH DURING THE FIRST 1–3 PACKS OF PILLS. If you feel sick to your stomach or have spotting or light bleeding, do not stop taking the pill. The problem will usually go away. If it doesn't go away, check with your healthcare professional.
4. MISSING PILLS CAN ALSO CAUSE SPOTTING OR LIGHT BLEEDING, even when you make up these missed pills.
  On the days you take 2 pills to make up for missed pills, you could also feel a little sick to your stomach.
5. IF YOU HAVE VOMITING OR DIARRHEA, OR IF YOU TAKE SOME MEDICINES, including some antibiotics, your pills may not work as well.
  Use a back-up method (such as a condom or spermicide) until you check with your healthcare professional.
6. IF YOU HAVE TROUBLE REMEMBERING TO TAKE THE PILL, talk to your healthcare professional about how to make pill-taking easier or about using another method of birth control.
7. IF YOU HAVE ANY QUESTIONS OR ARE UNSURE ABOUT THE INFORMATION IN THIS LEAFLET, call your healthcare professional.

BEFORE YOU START TAKING YOUR PILLS

1. DECIDE WHAT TIME OF DAY YOU WANT TO TAKE YOUR PILL.
  It is important to take it at about the same time every day.
2. LOOK AT YOUR PILL PACK:
  The pill pack has 21 "active" pills (with hormones) to take for 3 weeks. There are 7 white "active" pills, 7 light blue "active" pills, and 7 blue "active" pills. This is followed by 1 week of "reminder" dark green pills (without hormones).
3. ALSO FIND:
  1) where on the pack to start taking pills,
  2) in what order to take the pills.

CHECK PICTURE OF PILL PACK AND ADDITIONAL INSTRUCTIONS FOR USING THIS PACKAGE IN THE BRIEF SUMMARY PATIENT PACKAGE INSERT.

4. BE SURE YOU HAVE READY AT ALL TIMES:
  ANOTHER KIND OF BIRTH CONTROL (such as a condom or spermicide) to use as a back-up method in case you miss pills.
  AN EXTRA, FULL PILL PACK.

WHEN TO START THE FIRST PACK OF PILLS

You have a choice of which day to start taking your first pack of pills. TriNessa® is available in a blister card with a tablet dispenser which is preset for a Sunday Start. Day 1 Start is also provided. Decide with your healthcare professional which is the best day for you. Pick a time of day that will be easy to remember.

Sunday Start:

Take the first white "active" pill of the first pack on the Sunday after your period starts, even if you are still bleeding. If your period begins on Sunday, start the pack that same day.

Use another method of birth control such as a condom or spermicide as a back-up method if you have sex anytime from the Sunday you start your first pack until the next Sunday (7 days).

Day 1 Start:

Take the first white "active" pill of the first pack during the first 24 hours of your period.

You will not need to use a back-up method of birth control, since you are starting the pill at the beginning of your period.

WHAT TO DO DURING THE MONTH

1. Take One Pill at the Same Time Every Day Until the Pack is Empty.
  Do not skip pills even if you are spotting or bleeding between monthly periods or feel sick to your stomach (nausea).
  Do not skip pills even if you do not have sex very often.
2. When You Finish a Pack or Switch Your Brand of Pills:
  Start the next pack on the day after your last "reminder" pill. Do not wait any days between packs.

WHAT TO DO IF YOU MISS PILLS

If you MISS 1 white, light blue, or blue "active" pill:

1. Take it as soon as you remember. Take the next pill at your regular time. This means you may take 2 pills in 1 day.
2. You do not need to use a back-up birth control method if you have sex.

If you MISS 2 white or light blue "active" pills in a row in WEEK 1 OR WEEK 2 of your pack:

1. Take 2 pills on the day you remember and 2 pills the next day.
2. Then take 1 pill a day until you finish the pack.
3. You COULD BECOME PREGNANT if you have sex in the 7 days after you miss pills. You MUST use another birth control method (such as a condom or spermicide) as a back-up method for those 7 days.

If you MISS 2 blue "active" pills in a row in THE 3RD WEEK:

1. If you are a Sunday Starter:
  Keep taking 1 pill every day until Sunday. On Sunday, THROW OUT the rest of the pack and start a new pack of pills that same day.
  If you are a Day 1 Starter:
  THROW OUT the rest of the pill pack and start a new pack that same day.
2. You may not have your period this month but this is expected. However, if you miss your period 2 months in a row, call your healthcare professional because you might be pregnant.
3. You COULD BECOME PREGNANT if you have sex in the 7 days after you miss pills. You MUST use another birth control method (such as a condom or spermicide) as a back-up method for those 7 days.

If you MISS 3 OR MORE white, light blue, or blue "active" pills in a row (during the first 3 weeks):

1. If you are a Sunday Starter:
  Keep taking 1 pill every day until Sunday. On Sunday, THROW OUT the rest of the pack and start a new pack of pills that same day.
  If you are a Day 1 Starter:
  THROW OUT the rest of the pill pack and start a new pack that same day.
2. You may not have your period this month but this is expected. However, if you miss your period 2 months in a row, call your healthcare professional because you might be pregnant.
3. You COULD BECOME PREGNANT if you have sex in the 7 days after you miss pills. You MUST use another birth control method (such as a condom or spermicide) as a back-up method for those 7 days.

A REMINDER:

If you forget any of the 7 dark green "reminder" pills in WEEK 4:

THROW AWAY the pills you missed.

Keep taking 1 pill each day until the pack is empty.

You do not need a back-up method.

FINALLY, IF YOU ARE STILL NOT SURE WHAT TO DO ABOUT THE PILLS YOU HAVE MISSED:

Use a BACK-UP METHOD anytime you have sex.

KEEP TAKING ONE "ACTIVE" PILL EACH DAY until you can reach your healthcare professional.

PREGNANCY DUE TO PILL FAILURE

The incidence of pill failure resulting in pregnancy is approximately 5%, including women who do not always take the pills exactly as directed. If failure does occur, the risk to the fetus is minimal.

PREGNANCY AFTER STOPPING THE PILL

There may be some delay in becoming pregnant after you stop using oral contraceptives, especially if you had irregular menstrual cycles before you used oral contraceptives. It may be advisable to postpone conception until you begin menstruating regularly once you have stopped taking the pill and desire pregnancy.

There does not appear to be any increase in birth defects in newborn babies when pregnancy occurs soon after stopping the pill.

OVERDOSAGE

Serious ill effects have not been reported following ingestion of large doses of oral contraceptives by young children. Overdosage may cause nausea and withdrawal bleeding in females. In case of overdosage, contact your healthcare professional or pharmacist.

OTHER INFORMATION

Your healthcare professional will take a medical and family history before prescribing oral contraceptives and will examine you. The physical examination may be delayed to another time if you request it and the healthcare professional believes that it is a good medical practice to postpone it. You should be reexamined at least once a year. Be sure to inform your healthcare professional if there is a family history of any of the conditions listed previously in this leaflet. Be sure to keep all appointments with your healthcare professional, because this is a time to determine if there are early signs of side effects of oral contraceptive use.

Do not use the drug for any condition other than the one for which it was prescribed. This drug has been prescribed specifically for you; do not give it to others who may want birth control pills.

HEALTH BENEFITS FROM ORAL CONTRACEPTIVES

In addition to preventing pregnancy, use of combination oral contraceptives may provide certain benefits. They are:

- menstrual cycles may become more regular
- blood flow during menstruation may be lighter and less iron may be lost. Therefore, anemia due to iron deficiency is less likely to occur.
- pain or other symptoms during menstruation may be encountered less frequently
- ectopic (tubal) pregnancy may occur less frequently
- noncancerous cysts or lumps in the breast may occur less frequently
- acute pelvic inflammatory disease may occur less frequently
- oral contraceptive use may provide some protection against developing two forms of cancer: cancer of the ovaries and cancer of the lining of the uterus.

If you want more information about birth control pills, ask your healthcare professional or pharmacist. They have a more technical leaflet called the Professional Labeling, which you may wish to read. The professional labeling is also published in a book entitled Physicians' Desk Reference, available in many book stores and public libraries.

Keep out of reach of children.

Store at 25°C (77°F); excursions permitted to 15° – 30°C (59° – 86°F).

Protect from light.

WATSON (LOGO)

Mfd. for:

Watson Laboratories, Inc.

A Subsidiary of Watson Pharmaceuticals, Inc.

Corona, CA 92880 USA

Mfd.by:

JOLLC

Manati, Puerto Rico 00674

Revised September 2010

10304502

Printed in U.S.A.

Additional barcode labeling by:
Physicians Total Care, Inc.
Tulsa, Oklahoma 74146

PRINCIPAL DISPLAY PANEL - 28 Day Regimen Carton

NDC 54868-5826-0

TriNessa®
(norgestimate and ethinyl
estradiol tablets)

28-DAY REGIMEN

Each white tablet contains 0.180 mg norgestimate and 0.035 mg ethinyl
estradiol. Each light blue tablet contains 0.215 mg norgestimate and
0.035 mg ethinyl estradiol. Each blue tablet contains 0.250 mg norgestimate
and 0.035 mg ethinyl estradiol. Each green tablet contains inert ingredients.

Dispensers of 28 Tablets Each.

Rx only